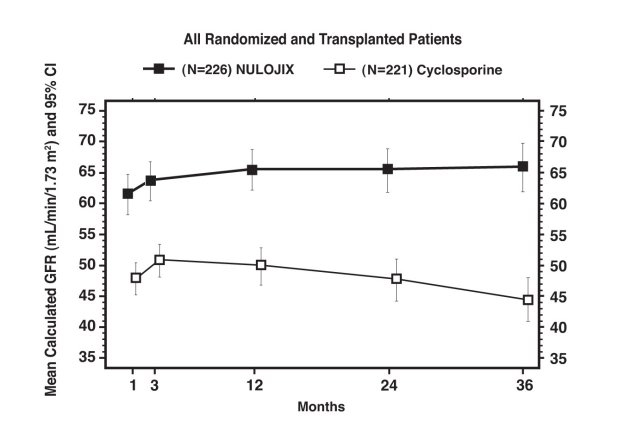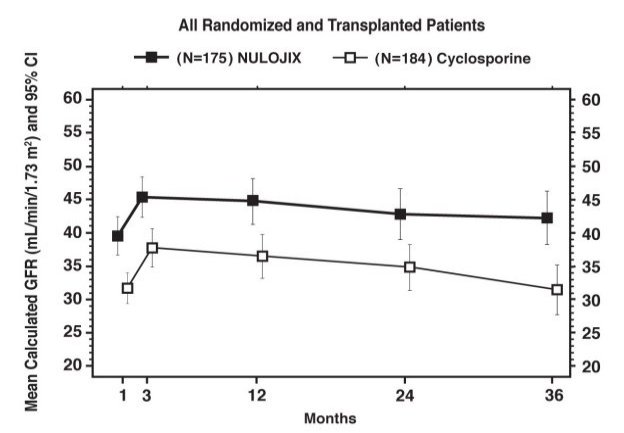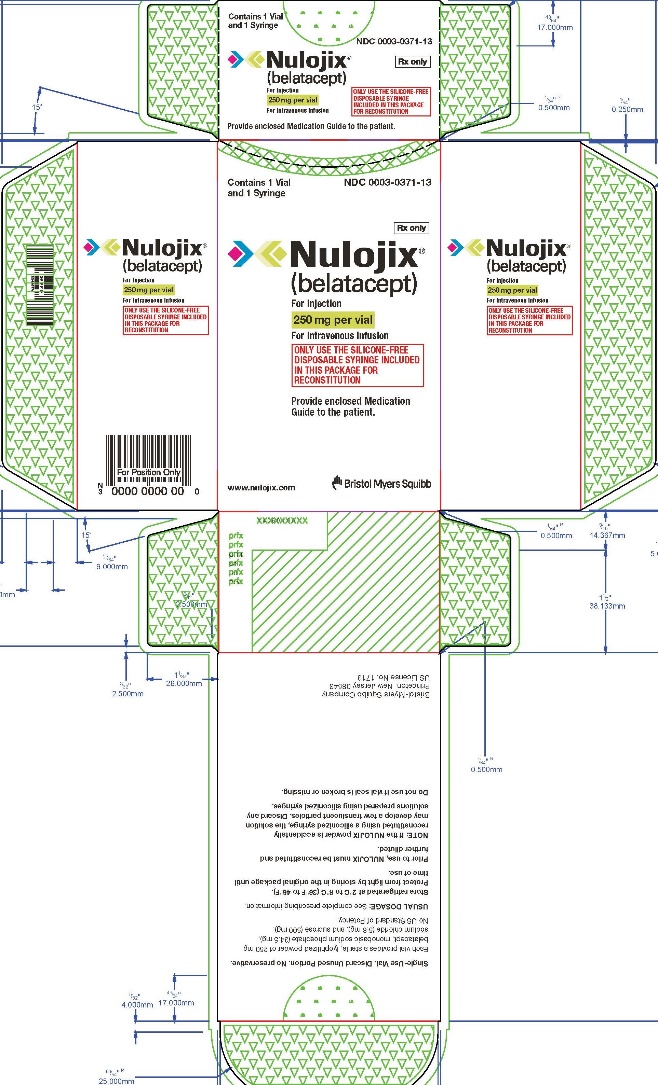 DRUG LABEL: NULOJIX
NDC: 0003-0371 | Form: INJECTION, POWDER, LYOPHILIZED, FOR SOLUTION
Manufacturer: E.R. Squibb & Sons, L.L.C.
Category: prescription | Type: HUMAN PRESCRIPTION DRUG LABEL
Date: 20210728

ACTIVE INGREDIENTS: belatacept 250 mg/1 1
INACTIVE INGREDIENTS: SODIUM PHOSPHATE, MONOBASIC, MONOHYDRATE 34.5 mg/1 1; sodium chloride 5.8 mg/1 1; sucrose 500 mg/1 1

HIGHLIGHTS OF PRESCRIBING INFORMATION

These highlights do not include all the information needed to use NULOJIX safely and effectively. See full prescribing information for NULOJIX.
NULOJIX (belatacept) for injection, for intravenous use
Initial U.S. Approval: 2011

RECENT MAJOR CHANGES

Warnings and Precautions (5.10) | 07/2021

WARNING: POST-TRANSPLANT LYMPHOPROLIFERATIVE DISORDER, OTHER MALIGNANCIES, AND SERIOUS INFECTIONS

See full prescribing information for complete boxed warning.

- Increased risk for developing post-transplant lymphoproliferative disorder (PTLD), predominantly involving the central nervous system (CNS). Recipients without immunity to Epstein-Barr virus (EBV) are at a particularly increased risk; therefore, use in EBV seropositive patients only. Do not use NULOJIX in transplant recipients who are EBV seronegative or with unknown serostatus. (4, 5.1)
- Only physicians experienced in immunosuppressive therapy and management of kidney transplant patients should prescribe NULOJIX. (5.2)
- Increased susceptibility to infection and the possible development of malignancies may result from immunosuppression. (5.1, 5.3, 5.4, 5.5)
- Use in liver transplant patients is not recommended due to an increased risk of graft loss and death. (5.6)

1 INDICATIONS AND USAGE

- NULOJIX is a selective T cell costimulation blocker indicated for prophylaxis of organ rejection in adult patients receiving a kidney transplant. (1.1)
- Use in combination with basiliximab induction, mycophenolate mofetil, and corticosteroids. (1.1)

Limitations of Use:

- Use only in patients who are EBV seropositive. (1.2, 4, 5.1)
- Use has not been established for the prophylaxis of organ rejection in transplanted organs other than the kidney. (1.2, 5.6)

2 DOSAGE AND ADMINISTRATION

- Use of higher than recommended or more frequent dosing is not recommended due to increased risk of serious infections and malignancy. (5.1, 5.4, 6.1)
- For complete dosing instructions, see full prescribing information. (2.1)

Dosing of NULOJIX for Kidney Transplant Recipients (2.1)
Dosing for Initial Phase | Dose
Day 1 (day of transplantation, prior to implantation) and Day 5 (approximately 96 hours after Day 1 dose) | 10 mg per kg
End of Week 2 and Week 4 after transplantation | 10 mg per kg
End of Week 8 and Week 12 after transplantation | 10 mg per kg
Dosing for Maintenance Phase | Dose
End of Week 16 after transplantation and every 4 weeks (plus or minus 3 days) thereafter | 5 mg per kg

- For intravenous infusion only; administer over 30 minutes. (2.1, 2.2)
- Only use the enclosed silicone-free disposable syringe to prepare for administration. (2.2)

3 DOSAGE FORMS AND STRENGTHS

Lyophilized powder for injection: 250 mg per vial (3)

4 CONTRAINDICATIONS

Patients who are EBV seronegative or with unknown EBV serostatus. (4)

5 WARNINGS AND PRECAUTIONS

- Post-Transplant Lymphoproliferative Disorder (PTLD): increased risk, predominantly involving the CNS; monitor for new or worsening neurological, cognitive, or behavioral signs and symptoms. (Boxed Warning, 4, 5.1, 5.6)
- Other malignancies: increased risk with all immunosuppressants; appears related to intensity and duration of use. Avoid prolonged exposure to UV light and sunlight. (5.3)
- Progressive Multifocal Leukoencephalopathy (PML): increased risk; consider in the diagnosis of patients reporting new or worsening neurological, cognitive, or behavioral signs and symptoms. Recommended doses of immunosuppressants should not be exceeded. (5.4)
- Other serious infections: increased risk of bacterial, viral, fungal, and protozoal infections, including opportunistic infections and tuberculosis. Some infections were fatal. Polyoma virus-associated nephropathy can lead to kidney graft loss; consider reduction in immunosuppression. Evaluate for tuberculosis and initiate treatment for latent infection prior to NULOJIX use. Cytomegalovirus and pneumocystis prophylaxis are recommended after transplantation. (5.1, 5.4, 5.5)
- Liver transplant: use is not recommended. (5.6)
- Acute Rejection and Graft Loss with Corticosteroid Minimization: corticosteroid utilization should be consistent with the NULOJIX clinical trial experience. (2.1, 5.7, 14.1)
- Immunizations: avoid use of live vaccines during treatment. (5.8)
- Coadministration with Anti-Thymocyte Globulin: in de novo kidney transplant recipients, especially those with other predisposing risk factors for venous thrombosis of the renal allograft, coadministration (at the same or nearly the same time) with anti-thymocyte globulin may pose a risk for venous thrombosis of the renal allograft. (5.9, 6.2, 7.3)
- Risk of Rejection with Conversion From a CNI Based Maintenance Regimen: conversion of maintenance kidney transplant recipients from a CNI based to NULOJIX based maintenance regimen increases the risk of acute rejection. Conversion of stable kidney transplant recipients from a CNI based maintenance therapy to a belatacept based maintenance therapy is not recommended unless the patient is CNI intolerant. (5.10)

6 ADVERSE REACTIONS

Most common adverse reactions (≥20% on NULOJIX treatment) are anemia, diarrhea, urinary tract infection, peripheral edema, constipation, hypertension, pyrexia, graft dysfunction, cough, nausea, vomiting, headache, hypokalemia, hyperkalemia, and leukopenia. (6.1)

To report SUSPECTED ADVERSE REACTIONS, contact Bristol-Myers Squibb at 1-800-721-5072 or FDA at 1-800-FDA-1088 or www.fda.gov/medwatch.

8 USE IN SPECIFIC POPULATIONS

- Pregnancy: Based on animal data, may cause fetal harm; pregnancy registry available. (8.1)
- Lactation: Discontinue drug or nursing, taking into consideration importance of drug to mother. (8.2)

FULL PRESCRIBING INFORMATION

WARNING: POST-TRANSPLANT LYMPHOPROLIFERATIVE DISORDER, OTHER MALIGNANCIES, AND SERIOUS INFECTIONS

Increased risk for developing post-transplant lymphoproliferative disorder (PTLD), predominantly involving the central nervous system (CNS). Recipients without immunity to Epstein-Barr virus (EBV) are at a particularly increased risk; therefore, use in EBV seropositive patients only. Do not use NULOJIX in transplant recipients who are EBV seronegative or with unknown EBV serostatus [see Contraindications (4) and Warnings and Precautions (5.1)].

Only physicians experienced in immunosuppressive therapy and management of kidney transplant patients should prescribe NULOJIX. Patients receiving the drug should be managed in facilities equipped and staffed with adequate laboratory and supportive medical resources. The physician responsible for maintenance therapy should have complete information requisite for the follow-up of the patient [see Warnings and Precautions (5.2)].

Increased susceptibility to infection and the possible development of malignancies may result from immunosuppression [see Warnings and Precautions (5.1, 5.3, 5.4, 5.5)].

Use in liver transplant patients is not recommended due to an increased risk of graft loss and death [see Warnings and Precautions (5.6)].

1 INDICATIONS AND USAGE

1.1 Adult Kidney Transplant Recipients

NULOJIX® (belatacept) is indicated for prophylaxis of organ rejection in adult patients receiving a kidney transplant. NULOJIX is to be used in combination with basiliximab induction, mycophenolate mofetil, and corticosteroids.

1.2 Limitations of Use

Use NULOJIX only in patients who are EBV seropositive [see Contraindications (4) and Warnings and Precautions (5.1)].

Use of NULOJIX for the prophylaxis of organ rejection in transplanted organs other than kidney has not been established [see Warnings and Precautions (5.6)].

2 DOSAGE AND ADMINISTRATION

2.1 Dosage in Adult Kidney Transplant Recipients

NULOJIX should be administered in combination with basiliximab induction, mycophenolate mofetil (MMF), and corticosteroids. In clinical trials the median (25th to 75th percentile) corticosteroid doses were tapered to approximately 15 mg (10 to 20 mg) per day by the first 6 weeks and remained at approximately 10 mg (5 to 10 mg) per day for the first 6 months post-transplant. Corticosteroid utilization should be consistent with the NULOJIX clinical trial experience [see Warnings and Precautions (5.7) and Clinical Studies (14.1)].

Due to an increased risk of post-transplant lymphoproliferative disorder (PTLD) predominantly involving the central nervous system (CNS), progressive multifocal leukoencephalopathy (PML), and serious CNS infections, administration of higher than the recommended doses or more frequent dosing of NULOJIX is not recommended [see Warnings and Precautions (5.1, 5.4, 5.5) and Adverse Reactions (6.1)].

NULOJIX is for intravenous infusion only. Patients do not require premedication prior to administration of NULOJIX.

Dosing instructions are provided in Table 1.

- The total infusion dose of NULOJIX should be based on the actual body weight of the patient at the time of transplantation, and should not be modified during the course of therapy, unless there is a change in body weight of greater than 10%.
- The prescribed dose of NULOJIX must be evenly divisible by 12.5 mg in order for the dose to be prepared accurately using the reconstituted solution and the silicone-free disposable syringe provided. Evenly divisible increments are 0, 12.5, 25, 37.5, 50, 62.5, 75, 87.5, and 100. For example:
  - A patient weighs 64 kg. The dose is 10 mg per kg.
  - Calculated Dose: 64 kg × 10 mg per kg = 640 mg
  - The closest doses evenly divisible by 12.5 mg below and above 640 mg are 637.5 mg and 650 mg.
  - The nearest dose to 640 mg is 637.5 mg.
  - Therefore, the actual prescribed dose for the patient should be 637.5 mg.

Table 1: Dosinga,b of NULOJIX for Kidney Transplant Recipients
Dosing for Initial Phase | Dose
Day 1 (day of transplantation, prior to implantation) and Day 5 (approximately 96 hours after Day 1 dose) | 10 mg per kg
End of Week 2 and Week 4 after transplantation | 10 mg per kg
End of Week 8 and Week 12 after transplantation | 10 mg per kg
Dosing for Maintenance Phase | Dose
End of Week 16 after transplantation and every 4 weeks (plus or minus 3 days) thereafter | 5 mg per kg
a [See Clinical Studies (14.1)]
b The dose prescribed for the patient must be evenly divisible by 12.5 mg (see instructions above; eg, evenly divisible increments are 0, 12.5, 25, 37.5, 50, 62.5, 75, 87.5, and 100).

2.2 Preparation and Administration Instructions

NULOJIX is for intravenous infusion only.

Caution: NULOJIX must be reconstituted/prepared using only the silicone-free disposable syringe provided with each vial.

If the silicone-free disposable syringe is dropped or becomes contaminated, use a new silicone-free disposable syringe from inventory.

Preparation for Administration

1. Calculate the number of NULOJIX vials required to provide the total infusion dose. Each vial contains 250 mg of belatacept lyophilized powder.
2. Reconstitute the contents of each vial of NULOJIX with 10.5 mL of a suitable diluent using the silicone-free disposable syringe provided with each vial and an 18- to 21-gauge needle. Suitable diluents include: sterile water for injection (SWFI), 0.9% sodium chloride (NS), or 5% dextrose in water (D5W).
  Note: If the NULOJIX powder is accidentally reconstituted using a different syringe than the one provided, the solution may develop a few translucent particles. Discard any solutions prepared using siliconized syringes.
3. To reconstitute the NULOJIX powder, remove the flip-top from the vial and wipe the top with an alcohol swab. Insert the syringe needle into the vial through the center of the rubber stopper and direct the stream of diluent (10.5 mL of SWFI, NS, or D5W) to the glass wall of the vial.
4. To minimize foam formation, rotate the vial and invert with gentle swirling until the contents are completely dissolved. Avoid prolonged or vigorous agitation. Do not shake.
5. The reconstituted solution contains a belatacept concentration of 25 mg/mL and should be clear to slightly opalescent and colorless to pale yellow. Do not use if opaque particles, discoloration, or other foreign particles are present.
6. Calculate the total volume of the reconstituted 25 mg/mL NULOJIX solution required to provide the total infusion dose.
  Volume of 25 mg/mL NULOJIX solution (in mL) = Prescribed Dose (in mg) ÷ 25 mg/mL
7. Prior to intravenous infusion, the required volume of the reconstituted NULOJIX solution must be further diluted with a suitable infusion fluid (NS or D5W). NULOJIX reconstituted with:
  1. SWFI should be further diluted with either NS or D5W
  2. NS should be further diluted with NS
  3. D5W should be further diluted with D5W
8. From the appropriate size infusion bag or bottle, withdraw a volume of infusion fluid that is equal to the volume of the reconstituted NULOJIX solution required to provide the prescribed dose. With the same silicone-free disposable syringe used for reconstitution, withdraw the required amount of belatacept solution from the vial, inject it into the infusion bag or bottle, and gently rotate the infusion bag or bottle to ensure mixing.
  The final belatacept concentration in the infusion bag or bottle should range from 2 mg/mL to 10 mg/mL. Typically, an infusion volume of 100 mL will be appropriate for most patients and doses, but total infusion volumes ranging from 50 mL to 250 mL may be used. Any unused solution remaining in the vials must be discarded.
9. Prior to administration, the NULOJIX infusion should be inspected visually for particulate matter and discoloration. Discard the infusion if any particulate matter or discoloration is observed.
10. The entire NULOJIX infusion should be administered over a period of 30 minutes and must be administered with an infusion set and a sterile, non-pyrogenic, low-protein-binding filter (with a pore size of 0.2 to 1.2 µm).
  1. The reconstituted solution should be transferred from the vial to the infusion bag or bottle immediately. The NULOJIX infusion must be completed within 24 hours of reconstitution of the NULOJIX lyophilized powder. If not used immediately, the infusion solution may be stored under refrigeration conditions: 2°C to 8°C (36°F to 46°F) and protected from light for up to 24 hours (a maximum of 4 hours of the total 24 hours can be at room temperature: 20°C to 25°C [68°F to 77°F] and room light).
  2. Infuse NULOJIX in a separate line from other concomitantly infused agents. NULOJIX should not be infused concomitantly in the same intravenous line with other agents. No physical or biochemical compatibility studies have been conducted to evaluate the coadministration of NULOJIX with other agents [see Warnings and Precautions (5.9)].

3 DOSAGE FORMS AND STRENGTHS

Lyophilized powder for injection: 250 mg per vial.

4 CONTRAINDICATIONS

NULOJIX is contraindicated in transplant recipients who are Epstein-Barr virus (EBV) seronegative or with unknown EBV serostatus due to the risk of post-transplant lymphoproliferative disorder (PTLD), predominantly involving the central nervous system (CNS) [see Boxed Warning and Warnings and Precautions (5.1)].

5 WARNINGS AND PRECAUTIONS

5.1 Post-Transplant Lymphoproliferative Disorder

NULOJIX-treated patients have an increased risk for developing post-transplant lymphoproliferative disorder (PTLD), predominantly involving the CNS, compared to patients on a cyclosporine-based regimen [see Adverse Reactions (6.1), Clinical Studies (14.2)]. As the total burden of immunosuppression is a risk factor for PTLD, higher than the recommended doses or more frequent dosing of NULOJIX and higher than recommended doses of concomitant immunosuppressive agents are not recommended [see Dosage and Administration (2.1) and Warnings and Precautions (5.6)]. Physicians should consider PTLD in patients reporting new or worsening neurological, cognitive, or behavioral signs or symptoms.

EBV Serostatus

The risk of PTLD was higher in EBV seronegative patients compared to EBV seropositive patients. EBV seropositive patients are defined as having evidence of acquired immunity shown by the presence of IgG antibodies to viral capsid antigen (VCA) and EBV nuclear antigen (EBNA).

Epstein-Barr virus serology should be ascertained before starting administration of NULOJIX, and only patients who are EBV seropositive should receive NULOJIX. Transplant recipients who are EBV seronegative, or with unknown serostatus, should not receive NULOJIX [see Boxed Warning and Contraindications (4)].

Other Risk Factors

Other known risk factors for PTLD include cytomegalovirus (CMV) infection and T cell-depleting therapy. T cell-depleting therapies to treat acute rejection should be used cautiously. CMV prophylaxis is recommended for at least 3 months after transplantation [see Warnings and Precautions (5.5)].

Patients who are EBV seropositive and CMV seronegative may be at increased risk for PTLD compared to patients who are EBV seropositive and CMV seropositive [see Adverse Reactions (6.1)]. Since CMV seronegative patients are at increased risk for CMV disease (a known risk factor for PTLD), the clinical significance of CMV serology for PTLD remains to be determined; however, these findings should be considered when prescribing NULOJIX.

5.2 Management of Immunosuppression

Only physicians experienced in management of systemic immunosuppressant therapy in transplantation should prescribe NULOJIX. Patients receiving the drug should be managed in facilities equipped and staffed with adequate laboratory and supportive medical resources. The physician responsible for the maintenance therapy should have complete information requisite for the follow-up of the patient [see Boxed Warning].

5.3 Other Malignancies

Patients receiving immunosuppressants, including NULOJIX, are at increased risk of developing malignancies, in addition to PTLD, including the skin [see Boxed Warning and Warnings and Precautions (5.1)]. Exposure to sunlight and ultraviolet (UV) light should be limited by wearing protective clothing and using a sunscreen with a high protection factor.

5.4 Progressive Multifocal Leukoencephalopathy

Progressive multifocal leukoencephalopathy (PML) is an often rapidly progressive and fatal opportunistic infection of the CNS that is caused by the JC virus, a human polyoma virus. In clinical trials with NULOJIX, two cases of PML were reported in patients receiving NULOJIX at higher cumulative doses and more frequently than the recommended regimen, along with mycophenolate mofetil (MMF) and corticosteroids; one case occurred in a kidney transplant recipient and the second case occurred in a liver transplant recipient [see Warnings and Precautions (5.6), Adverse Reactions (6.1), Clinical Studies (14.2)]. As PML has been associated with high levels of overall immunosuppression, the recommended doses and frequency of NULOJIX and concomitant immunosuppressives, including MMF, should not be exceeded.

Physicians should consider PML in the differential diagnosis in patients with new or worsening neurological, cognitive, or behavioral signs or symptoms. PML is usually diagnosed by brain imaging, cerebrospinal fluid (CSF) testing for JC viral DNA by polymerase chain reaction (PCR), and/or brain biopsy. Consultation with a specialist (eg, neurologist and/or infectious disease) should be considered for any suspected or confirmed cases of PML.

If PML is diagnosed, consideration should be given to reduction or withdrawal of immunosuppression taking into account the risk to the allograft.

5.5 Other Serious Infections

Patients receiving immunosuppressants, including NULOJIX, are at increased risk of developing bacterial, viral (cytomegalovirus [CMV] and herpes), fungal, and protozoal infections, including opportunistic infections. These infections may lead to serious, including fatal, outcomes [see Boxed Warning and Adverse Reactions (6.1)].

Prophylaxis for cytomegalovirus is recommended for at least 3 months after transplantation. Prophylaxis for Pneumocystis jiroveci is recommended after transplantation.

Tuberculosis

Tuberculosis was more frequently observed in patients receiving NULOJIX than cyclosporine in clinical trials [see Adverse Reactions (6.1)]. Patients should be evaluated for tuberculosis and tested for latent infection prior to initiating NULOJIX. Treatment of latent tuberculosis infection should be initiated prior to NULOJIX use.

Polyoma Virus Nephropathy

In addition to cases of JC virus-associated PML [see Warnings and Precautions (5.4)], cases of polyoma virus-associated nephropathy (PVAN), mostly due to BK virus infection, have been reported. PVAN is associated with serious outcomes; including deteriorating renal function and kidney graft loss [see Adverse Reactions (6.1)]. Patient monitoring may help detect patients at risk for PVAN. Reductions in immunosuppression should be considered for patients who develop evidence of PVAN. Physicians should also consider the risk that reduced immunosuppression represents to the functioning allograft.

5.6 Liver Transplant

Use of NULOJIX in liver transplant patients is not recommended [see Boxed Warning]. In a clinical trial of liver transplant patients, use of NULOJIX regimens with more frequent administration of belatacept than any of those studied in kidney transplant, along with mycophenolate mofetil (MMF) and corticosteroids, was associated with a higher rate of graft loss and death compared to the tacrolimus control arms. In addition, two cases of PTLD involving the liver allograft (one fatal) and one fatal case of PML were observed among the 147 patients randomized to NULOJIX. The two cases of PTLD were reported among the 140 EBV seropositive patients (1.4%). The fatal case of PML was reported in a patient receiving higher than recommended doses of NULOJIX and MMF [see Warnings and Precautions (5.4)].

5.7 Acute Rejection and Graft Loss with Corticosteroid Minimization

In postmarketing experience, use of NULOJIX in conjunction with basiliximab induction, MMF, and corticosteroid minimization to 5 mg per day between Day 3 and Week 6 post-transplant was associated with an increased rate and grade of acute rejection, particularly Grade III rejection. These Grade III rejections occurred in patients with 4 to 6 HLA mismatches. Graft loss was a consequence of Grade III rejection in some patients.

Corticosteroid utilization should be consistent with the NULOJIX clinical trial experience [see Dosage and Administration (2.1) and Clinical Studies (14.1)].

5.8 Immunizations

The use of live vaccines should be avoided during treatment with NULOJIX, including but not limited to the following: intranasal influenza, measles, mumps, rubella, oral polio, BCG, yellow fever, varicella, and TY21a typhoid vaccines.

5.9 Coadministration with Anti-Thymocyte Globulin

In postmarketing experience in de novo kidney transplant recipients, some with other predisposing risk factors for venous thrombosis of the renal allograft, venous thrombosis of the renal allograft has occurred when the initial dose of anti-thymocyte globulin, as immunosuppressive induction, was coadministered (at the same or nearly the same time) with the first dose of belatacept. In such patients, the coadministration (at the same or nearly the same time) of anti-thymocyte globulin and belatacept may pose a risk for venous thrombosis of the renal allograft. If anti-thymocyte globulin (or any other cell-depleting induction treatment) and belatacept will be administered concomitantly, a twelve-hour interval between the two administrations is suggested.

5.10 Risk of Rejection with Conversion From a CNI Based Maintenance Regimen

Conversion of patients receiving a CNI based maintenance regimen to a NULOJIX based maintenance regimen increases the risk of acute rejection. In two randomized controlled studies, kidney transplant recipients at least six months post-transplant and stable on a CNI based regimen who were converted to a belatacept based regimen experienced higher rejection rates mostly during the first year post-conversion than patients maintained on their CNI based regimens. Conversion of stable kidney transplant recipients from a CNI based maintenance therapy to a belatacept based maintenance therapy is not recommended unless the patient is CNI intolerant.

6 ADVERSE REACTIONS

The most serious adverse reactions reported with NULOJIX are:

- PTLD, predominantly CNS PTLD, and other malignancies [see Boxed Warning and Warnings and Precautions (5.1, 5.3)]
- Serious infections, including JC virus-associated PML and polyoma virus nephropathy [see Warnings and Precautions (5.4, 5.5, 5.6)]

6.1 Clinical Studies Experience

Because clinical trials are conducted under widely varying conditions, the adverse reaction rates observed cannot be directly compared to rates in other trials and may not reflect the rates observed in clinical practice.

The data described below primarily derive from two randomized, active-controlled three-year trials of NULOJIX in de novo kidney transplant patients. In Study 1 and Study 2, NULOJIX was studied at the recommended dose and frequency [see Dosage and Administration (2.1)] in a total of 401 patients compared to a cyclosporine control regimen in a total of 405 patients. These two trials also included a total of 403 patients treated with a NULOJIX regimen of higher cumulative dose and more frequent dosing than recommended [see Clinical Studies (14.1)]. All patients also received basiliximab induction, mycophenolate mofetil, and corticosteroids. Patients were treated and followed for three years.

CNS PTLD, PML, and other CNS infections were more frequently observed in association with a NULOJIX regimen of higher cumulative dose and more frequent dosing compared to the recommended regimen; therefore, administration of higher than the recommended doses and/or more frequent dosing of NULOJIX is not recommended [see Dosage and Administration (2.1), Clinical Studies (14.2)].

The average age of patients in Studies 1 and 2 in the NULOJIX recommended dose and cyclosporine control regimens was 49 years, ranging from 18 to 79 years. Approximately 70% of patients were male; 67% were white, 11% were black, and 22% other races. About 25% of patients were from the United States and 75% from other countries.

The most commonly reported adverse reactions occurring in ≥20% of patients treated with the recommended dose and frequency of NULOJIX were anemia, diarrhea, urinary tract infection, peripheral edema, constipation, hypertension, pyrexia, graft dysfunction, cough, nausea, vomiting, headache, hypokalemia, hyperkalemia, and leukopenia.

The proportion of patients who discontinued treatment due to adverse reactions was 13% for the recommended NULOJIX regimen and 19% for the cyclosporine control arm through three years of treatment. The most common adverse reactions leading to discontinuation in NULOJIX-treated patients were cytomegalovirus infection (1.5%) and complications of transplanted kidney (1.5%).

Information on selected significant adverse reactions observed during clinical trials is summarized below.

Post-Transplant Lymphoproliferative Disorder

Reported cases of post-transplant lymphoproliferative disorder (PTLD) up to 36 months post-transplant were obtained for NULOJIX by pooling both dosage regimens of NULOJIX in Studies 1 and 2 (804 patients) with data from a third study in kidney transplantation (Study 3, 145 patients) which evaluated two NULOJIX dosage regimens similar, but slightly different, from those of Studies 1 and 2 (see Table 2). The total number of NULOJIX patients from these three studies (949) was compared to the pooled cyclosporine control groups from all three studies (476 patients).

Among 401 patients in Studies 1 and 2 treated with the recommended regimen of NULOJIX and the 71 patients in Study 3 treated with a very similar (but non-identical) NULOJIX regimen, there were 5 cases of PTLD: 3 in EBV seropositive patients and 2 in EBV seronegative patients. Two of the 5 cases presented with CNS involvement.

Among the 477 patients in Studies 1, 2, and 3 treated with the NULOJIX regimen of higher cumulative dose and more frequent dosing than recommended, there were 8 cases of PTLD: 2 in EBV seropositive patients and 6 in EBV seronegative or serostatus unknown patients. Six of the 8 cases presented with CNS involvement. Therefore, administration of higher than the recommended doses or more frequent dosing of NULOJIX is not recommended [see Dosage and Administration (2.1) and Warnings and Precautions (5.1)].

One of the 476 patients treated with cyclosporine developed PTLD, without CNS involvement.

All cases of PTLD reported up to 36 months post-transplant in NULOJIX- or cyclosporine-treated patients presented within 18 months of transplantation.

Overall, the rate of PTLD in 949 patients treated with any of the NULOJIX regimens was 9-fold higher in those who were EBV seronegative or EBV serostatus unknown (8/139) compared to those who were EBV seropositive (5/810 patients). Therefore NULOJIX is recommended for use only in patients who are EBV seropositive [see Boxed Warning and Contraindications (4)].

Table 2: Summary of PTLD Reported in Studies 1, 2, and 3 Through Three Years of Treatment
 | NULOJIX Nonrecommended Regimena (N=477) |  |  | NULOJIX Recommended Regimenb (N=472) |  |  | Cyclosporine (N=476)
Trial | EBV Positive (n=406) | EBV Negative (n=43) | EBV Unknown (n=28) | EBV Positive (n=404) | EBV Negative (n=48) | EBV Unknown (n=20) | EBV Positive (n=399) | EBV Negative (n=57) | EBV Unknown (n=20)
Study 1
CNS PTLD | 1 | 1
Non-CNS PTLD |  | 1 |  | 2 |  |  |  | 1
Study 2
CNS PTLD | 1 | 1 |  | 1 | 1
Non-CNS PTLD |  |  |  |  | 1
Study 3
CNS PTLD |  | 2
Non-CNS PTLD |  |  | 1
Total (%) | 2 (0.5) | 5 (11.6) | 1 (3.6) | 3 (0.7) | 2 (4.1) | 0 | 0 | 1 (1.8) | 0
a Regimen with higher cumulative dose and more frequent dosing than the recommended NULOJIX regimen.
b In Studies 1 and 2 the NULOJIX regimen is identical to the recommended regimen, but is slightly different in Study 3.

PTLD in EBV Seropositive Subpopulation

Among the 806 EBV seropositive patients with known CMV serostatus treated with either NULOJIX regimen in Studies 1, 2, and 3, 2% (4/210) of CMV seronegative patients developed PTLD compared to 0.2% (1/596) of CMV seropositive patients. Among the 404 EBV seropositive recipients treated with the recommended dosage regimen of NULOJIX, 3 PTLD cases were detected among 99 CMV seronegative patients (3%) and there was no case detected among 303 CMV seropositive patients. The clinical significance of CMV serology as a risk factor for PTLD remains to be determined; however, these findings should be considered when prescribing NULOJIX [see Warnings and Precautions (5.1)].

Other Malignancies

Malignancies, excluding non-melanoma skin cancer and PTLD, were reported in Study 1 and Study 2 in 3.5% (14/401) of patients treated with the recommended NULOJIX regimen and 3.7% (15/405) of patients treated with the cyclosporine control regimen. Non-melanoma skin cancer was reported in 1.5% (6/401) of patients treated with the recommended NULOJIX regimen and in 3.7% (15/405) of patients treated with cyclosporine [see Warnings and Precautions (5.3)].

Progressive Multifocal Leukoencephalopathy

Two fatal cases of progressive multifocal leukoencephalopathy (PML) have been reported among 1096 patients treated with a NULOJIX-containing regimen: 1 patient in clinical trials of kidney transplant (Studies 1, 2, and 3 described above) and 1 patient in a trial of liver transplant (trial of 250 patients). No cases of PML were reported in patients treated with the recommended NULOJIX regimen or the control regimen in these trials.

The kidney transplant recipient was treated with the NULOJIX regimen of higher cumulative dose and more frequent dosing than recommended, mycophenolate mofetil (MMF), and corticosteroids for two years. The liver transplant recipient was treated with 6 months of a NULOJIX dosage regimen that was more intensive than that studied in kidney transplant recipients, MMF at doses higher than the recommended dose, and corticosteroids [see Warnings and Precautions (5.4)].

Bacterial, Mycobacterial, Viral, and Fungal Infections

Adverse reactions of infectious etiology were reported based on clinical assessment by physicians. The causative organisms for these reactions are identified when provided by the physician. The overall number of infections, serious infections, and select infections with identified etiology reported in patients treated with the NULOJIX recommended regimen or the cyclosporine control in Studies 1 and 2 are shown in Table 3. Fungal infections were reported in 18% of patients receiving NULOJIX compared to 22% receiving cyclosporine, primarily due to skin and mucocutaneous fungal infections. Tuberculosis and herpes infections were reported more frequently in patients receiving NULOJIX than cyclosporine. Of the patients who developed tuberculosis through three years, all but one NULOJIX patient lived in countries with a high prevalence of tuberculosis [see Warnings and Precautions (5.5)].

Table 3: Overall Infections and Select Infections with Identified Etiology by Treatment Group Following One and Three Years of Treatment in Studies 1 and 2a
 | Up to Year 1 |  | Up to Year 3b
 | NULOJIX Recommended Regimen N=401 n (%) | Cyclosporine N=405 n (%) | NULOJIX Recommended Regimen N=401 n (%) | Cyclosporine N=405 n (%)
All infectionsc | 287 (72) | 299 (74) | 329 (82) | 327 (81)
Serious infectionsd | 98 (24) | 113 (28) | 144 (36) | 157 (39)
CMV | 44 (11) | 52 (13) | 53 (13) | 56 (14)
Polyoma viruse | 10 (3) | 23 (6) | 17 (4) | 27 (7)
Herpesf | 27 (7) | 26 (6) | 55 (14) | 46 (11)
Tuberculosis | 2 (1) | 1 (<1) | 6 (2) | 1 (<1)
a Studies 1 and 2 were not designed to support comparative claims for NULOJIX for the adverse reactions reported in this table.
b Median exposure in days for pooled studies: 1203 for NULOJIX recommended regimen and 1163 for cyclosporine in Studies 1 and 2.
c All infections include bacterial, viral, fungal, and other organisms. For infectious adverse reactions, the causative organism is reported if specified by the physician in the clinical trials.
d A medically important event that may be life-threatening or result in death or hospitalization or prolongation of existing hospitalization. Infections not meeting these criteria are considered non-serious.
e BK virus-associated nephropathy was reported in 6 NULOJIX patients (4 of which resulted in graft loss) and 6 cyclosporine patients (none of which resulted in graft loss) by Year 3.
f Most herpes infections were non-serious and 1 led to treatment discontinuation.

Infections Reported in the CNS

Following three years of treatment in Studies 1 and 2, cryptococcal meningitis was reported in 1 patient out of 401 patients treated with the NULOJIX recommended regimen (0.2%) and 1 patient out of the 405 treated with the cyclosporine control (0.2%).

Six patients out of the 403 who were treated with the NULOJIX regimen of higher cumulative dose and more frequent dosing than recommended in Studies 1 and 2 (1.5%) were reported to have developed CNS infections, including 2 cases of cryptococcal meningitis, 1 case of Chagas encephalitis with cryptococcal meningitis, 1 case of cerebral aspergillosis, 1 case of West Nile encephalitis, and 1 case of PML (discussed above).

Infusion Reactions

There have been no reports of anaphylaxis or drug hypersensitivity in patients treated with NULOJIX in Studies 1 and 2 with up to three years of follow-up. However, milder infusion-related reactions within one hour of infusion were reported in 5% of patients treated with the recommended dose of NULOJIX, similar to the placebo rate. The most frequent reactions were hypotension and hypertension. A case of anaphylaxis was reported in the postmarketing experience [see Adverse Reactions (6.2)].

Proteinuria

At Month 1 after transplantation in Studies 1 and 2, the frequency of 2+ proteinuria on urine dipstick in patients treated with the NULOJIX recommended regimen was 33% (130/390) and 28% (107/384) in patients treated with the cyclosporine control regimen. The frequency of 2+ proteinuria was similar between the two treatment groups between one and three years after transplantation (<10% in both studies). There were no differences in the occurrence of 3+ proteinuria (<4% in both studies) at any time point, and no patients experienced 4+ proteinuria. The clinical significance of this increase in early proteinuria is unknown.

Immunogenicity

Antibodies directed against the belatacept molecule were assessed in 398 patients treated with the NULOJIX recommended regimen in Studies 1 and 2 (212 of these patients were treated for at least two years). Of the 372 patients with immunogenicity assessment at baseline (prior to receiving belatacept treatment), 29 patients tested positive for anti-belatacept antibodies; 13 of these patients had antibodies to the modified cytotoxic T lymphocyte-associated antigen 4 (CTLA-4). Anti-belatacept antibody titers did not increase during treatment in these 29 patients.

Eight (2%) patients developed antibodies during treatment with the NULOJIX recommended regimen. In the patients who developed antibodies during treatment, the median titer (by dilution method) was 8, with a range of 5 to 80. Of 56 patients who tested negative for antibodies during treatment and reassessed approximately 7 half-lives after discontinuation of NULOJIX, 1 tested antibody positive. Anti-belatacept antibody development was not associated with altered clearance of belatacept.

Samples from 6 patients with confirmed binding activity to the modified cytotoxic T lymphocyte-associated antigen 4 (CTLA-4) region of the belatacept molecule were assessed by an in vitro bioassay for the presence of neutralizing antibodies. Three of these 6 patients tested positive for neutralizing antibodies. However, the development of neutralizing antibodies may be underreported due to lack of assay sensitivity.

The clinical impact of anti-belatacept antibodies (including neutralizing anti-belatacept antibodies) could not be determined in the studies.

The data reflect the percentage of patients whose test results were positive for antibodies to belatacept in specific assays. The observed incidence of antibody (including neutralizing antibody) positivity in an assay may be influenced by several factors including assay sensitivity and specificity, assay methodology, sample handling, timing of sample collection, concomitant medications, and underlying disease. For these reasons, comparison of the incidence of antibodies to belatacept with the incidence of antibodies to other products may be misleading.

New-Onset Diabetes After Transplantation

The incidence of new-onset diabetes after transplantation (NODAT) was defined in Studies 1 and 2 as use of an antidiabetic agent for ≥30 days or ≥2 fasting plasma glucose values ≥126 mg/dL (7.0 mmol/L) post-transplantation. Of the patients treated with the NULOJIX recommended regimen, 5% (14/304) developed NODAT by the end of one year compared to 10% (27/280) of patients on the cyclosporine control regimen. However, by the end of the third year, the cumulative incidence of NODAT was 8% (24/304) in patients treated with the NULOJIX recommended regimen and 10% (29/280) in patients treated with the cyclosporine regimen.

Hypertension

Blood pressure and use of antihypertensive medications were reported in Studies 1 and 2. By Year 3, one or more antihypertensive medications were used in 85% of NULOJIX-treated patients and 92% of cyclosporine-treated patients. At one year after transplantation, systolic blood pressures were 8 mmHg lower and diastolic blood pressures were 3 mmHg lower in patients treated with the NULOJIX recommended regimen compared to the cyclosporine control regimen. At three years after transplantation, systolic blood pressures were 6 mmHg lower and diastolic blood pressures were 3 mmHg lower in NULOJIX-treated patients compared to cyclosporine-treated patients. Hypertension was reported as an adverse reaction in 32% of NULOJIX-treated patients and 37% of cyclosporine-treated patients (see Table 4).

Dyslipidemia

Mean values of total cholesterol, HDL, LDL, and triglycerides were reported in Studies 1 and 2. At one year after transplantation these values were 183 mg/dL, 50 mg/dL, 102 mg/dL, and 151 mg/dL, respectively, in 401 patients treated with the NULOJIX recommended regimen and 196 mg/dL, 48 mg/dL, 108 mg/dL, and 195 mg/dL, respectively, in 405 patients treated with the cyclosporine control regimen. At three years after transplantation, the total cholesterol, HDL, LDL, and triglycerides were 176 mg/dL, 49 mg/dL, 100 mg/dL, and 141 mg/dL, respectively, in NULOJIX-treated patients compared to 193 mg/dL, 48 mg/dL, 106 mg/dL, and 180 mg/dL in cyclosporine-treated patients.

The clinical significance of the lower mean triglyceride values in NULOJIX-treated patients at one and three years is unknown.

Other Adverse Reactions

Adverse reactions that occurred at a frequency of ≥10% in patients treated with the NULOJIX recommended regimen or cyclosporine control regimen in Studies 1 and 2 through three years are summarized by preferred term in decreasing order of frequency within Table 4.

Table 4: Adverse Reactions Reported by ≥10% of Patients Treated with Either the NULOJIX Recommended Regimen or Control in Studies 1 and 2 Through Three Yearsa,b
Adverse Reaction | NULOJIX Recommended Regimen N=401 % | Cyclosporine N=405 %
Infections and Infestations
Urinary tract infection | 37 | 36
Upper respiratory infection | 15 | 16
Nasopharyngitis | 13 | 16
Cytomegalovirus infection | 12 | 12
Influenza | 11 | 8
Bronchitis | 10 | 7
Gastrointestinal Disorders
Diarrhea | 39 | 36
Constipation | 33 | 35
Nausea | 24 | 27
Vomiting | 22 | 20
Abdominal pain | 19 | 16
Abdominal pain upper | 9 | 10
Metabolism and Nutrition Disorders
Hyperkalemia | 20 | 20
Hypokalemia | 21 | 14
Hypophosphatemia | 19 | 13
Dyslipidemia | 19 | 24
Hyperglycemia | 16 | 17
Hypocalcemia | 13 | 11
Hypercholesterolemia | 11 | 11
Hypomagnesemia | 7 | 10
Hyperuricemia | 5 | 12
Procedural Complications
Graft dysfunction | 25 | 34
General Disorders
Peripheral edema | 34 | 42
Pyrexia | 28 | 26
Blood and Lymphatic System Disorders
Anemia | 45 | 44
Leukopenia | 20 | 23
Renal and Urinary Disorders
Hematuria | 16 | 18
Proteinuria | 16 | 12
Dysuria | 11 | 11
Renal tubular necrosis | 9 | 13
Vascular Disorders
Hypertension | 32 | 37
Hypotension | 18 | 12
Respiratory, Thoracic, and Mediastinal Disorders
Cough | 24 | 18
Dyspnea | 12 | 15
Investigations
Blood creatinine increased | 15 | 20
Musculoskeletal and Connective Tissue Disorders
Arthralgia | 17 | 13
Back pain | 13 | 13
Nervous System Disorders
Headache | 21 | 18
Dizziness | 9 | 10
Tremor | 8 | 17
Skin and Subcutaneous Tissue Disorders
Acne | 8 | 11
Psychiatric Disorders
Insomnia | 15 | 18
Anxiety | 10 | 11
a All randomized and transplanted patients in Studies 1 and 2.
b Studies 1 and 2 were not designed to support comparative claims for NULOJIX for the adverse reactions reported in this table.

Selected adverse reactions occurring in <10% from NULOJIX-treated patients in either regimen through three years in Studies 1 and 2 are listed below:

Immune System Disorders: Guillain-Barré syndrome

Infections and Infestations: see Table 3

Gastrointestinal Disorders: stomatitis, including aphthous stomatitis

Injury, Poisoning, and Procedural Complications: chronic allograft nephropathy, complications of transplanted kidney, including wound dehiscence, arteriovenous fistula thrombosis

Blood and Lymphatic System Disorders: neutropenia

Renal and Urinary Disorders: renal impairment, including acute renal failure, renal artery stenosis, urinary incontinence, hydronephrosis

Vascular Disorders: hematoma, lymphocele

Musculoskeletal and Connective Tissue Disorders: musculoskeletal pain

Skin and Subcutaneous Tissue Disorders: alopecia, hyperhidrosis

Cardiac Disorders: atrial fibrillation

6.2 Postmarketing Experience

Because these reactions are reported voluntarily from a population of uncertain size, it is not always possible to reliably estimate their frequency or establish a causal relationship to drug exposure.

Immune System Disorder: Anaphylaxis

Spontaneous reports during the postmarketing experience included a case of anaphylaxis, which was observed in a kidney transplant patient whose belatacept therapy had been interrupted for two months during treatment of a systemic varicella infection. When belatacept therapy was resumed, within five minutes after the start of the belatacept infusion the patient developed a generalized rash, pruritus, hypotension, atrial fibrillation, respiratory distress, and syncope, requiring medical treatment. Another belatacept infusion was attempted one month later, but was terminated when the patient experienced more pronounced symptoms of anaphylaxis and required medical treatment.

Vascular Disorder: Venous Thrombosis of the Renal Allograft

In postmarketing experience in de novo kidney transplant recipients, some with other predisposing risk factors for venous thrombosis of the renal allograft, venous thrombosis of the renal allograft has occurred when the initial dose of anti-thymocyte globulin, as immunosuppressive induction, was coadministered (at the same or nearly the same time) with the first dose of belatacept [see Warnings and Precautions (5.9)].

6.3 Long-Term Extension Studies

After completion of the 36-month studies, patients remaining on randomized therapy in Study 1 and Study 2 were eligible for enrollment in the long-term extension studies [see Clinical Studies (14.2, 14.3)]. No new adverse reactions were observed in the extension studies.

7 DRUG INTERACTIONS

7.1 Mycophenolate Mofetil (MMF)

Monitor for a need to adjust concomitant mycophenolate mofetil (MMF) dosage when a patient’s therapy is switched between cyclosporine and NULOJIX, as cyclosporine decreases mycophenolic acid (MPA) exposure by preventing enterohepatic recirculation of MPA while NULOJIX does not [see Clinical Pharmacology (12.3)]:

- A higher MMF dosage may be needed after switching from NULOJIX to cyclosporine, since this may result in lower MPA concentrations and increase the risk of graft rejection.
- A lower MMF dosage may be needed after switching from cyclosporine to NULOJIX, since this may result in higher MPA concentrations and increase the risk for adverse reactions related to MPA (review the Full Prescribing Information for MMF).

7.2 Cytochrome P450 Substrates

No dosage adjustments are needed for drugs metabolized via CYP1A2, CYP2C9, CYP2D6, CYP3A, and CYP2C19 when coadministered with NULOJIX [see Clinical Pharmacology (12.3)].

7.3 Anti-Thymocyte Globulin

Coadministration (at the same or nearly the same time) of anti-thymocyte globulin (or any other cell-depleting induction treatment) and belatacept in de novo kidney transplant recipients, especially those with other predisposing risk factors for venous thrombosis of the renal allograft, may pose a risk for venous thrombosis of the renal allograft [see Warnings and Precautions (5.9)].

8 USE IN SPECIFIC POPULATIONS

8.1 Pregnancy

Pregnancy Exposure Registry

To monitor maternal-fetal outcomes of pregnant women who have received immunosuppressants including NULOJIX or whose partners have received NULOJIX, healthcare providers are strongly encouraged to register pregnant patients in the Transplant Pregnancy Registry International (TPR) by calling 1-877-955-6877.

Risk Summary

The data with NULOJIX use in pregnant women are insufficient to inform on drug-associated risk. Belatacept is known to cross the placenta of animals. Administration of belatacept to pregnant rats and rabbits during the period of organogenesis was not teratogenic at exposures approximately 16 and 19 times greater than that observed at the maximum recommended human dose (MRHD) of 10 mg per kg body weight administered over the first month of treatment, based on area under the concentration-time curve (AUC). In a pre- and postnatal development study in rats, treatment-related infections in dams were associated with increased pup mortality, presumably secondary to deteriorating maternal health, at exposures 3 times higher than that observed at MRHD [see Animal Data].

The background risk of major birth defects and miscarriage for the indicated population is unknown; however, in the U.S. general population, the estimated background risk of major birth defects is 2 to 4% and of miscarriage is 15 to 20% of clinically recognized pregnancies.

Data

Animal Data

In embryo-fetal development studies, daily intravenous administration of belatacept to pregnant rats and rabbits throughout the period of organogenesis did not produce adverse fetal effects at doses up to 200 mg per kg and 100 mg per kg, respectively (16 and 19 times the MRHD exposure, based on AUC). In a pre- and postnatal development study, daily intravenous administration of belatacept to rats from Day 6 of gestation through Day 20 of the lactation period was associated with maternal toxicity (infections) in a small percentage of dams at doses ≥20 mg per kg (3 times the MRHD exposure, based on AUC) resulting in increased pup mortality (up to 100% pup mortality in some dams). In pups that survived, there were no abnormalities or malformations at doses up to 200 mg per kg (19 times the MRHD exposure, based on AUC).

In vitro data indicate that belatacept has lower binding affinity to CD80/CD86 and lower potency in rodents than in humans. Although the rat toxicity studies with belatacept were done at pharmacologically saturating doses, the in vivo difference in potency between rats and humans is unknown. Therefore, the relevance of the rat toxicities to humans and the significance of the magnitude of the relative exposures (rats:humans) are unknown.

Abatacept, a fusion protein that differs from belatacept by two amino acids, binds to the same ligands (CD80/CD86) and blocks T cell costimulation like belatacept, but is more active than belatacept in rodents. Therefore, toxicities identified with abatacept in rodents, including infections and autoimmunity, may be predictive of adverse effects in humans treated with belatacept [see Nonclinical Toxicology (13.2)].

Autoimmunity was observed in 1 rat offspring exposed to abatacept in utero and/or during lactation and in juvenile rats after treatment with abatacept. However, the clinical relevance of autoimmunity in rats to patients or a fetus exposed in utero is unknown [see Nonclinical Toxicology (13.2)].

8.2 Lactation

Risk Summary

There are no data on the presence of NULOJIX in human milk or the effects of NULOJIX on breastfed infants or human milk production to inform risk of NULOJIX to an infant during lactation. Belatacept is excreted in rat milk after intravenous administration, and it is possible that the drug will be present in human milk. However, absorption of intact belatacept from the nursing infant’s gastrointestinal tract has not been studied. The developmental and health benefits of breastfeeding should be considered along with the mother’s clinical need for NULOJIX and any potential adverse effects on the breastfed child from NULOJIX or from the underlying maternal conditions.

8.4 Pediatric Use

The safety and efficacy of NULOJIX in patients under 18 years of age have not been established. Because T cell development continues into the teenage years, the potential concern for autoimmunity in neonates applies to pediatric use as well [see Use in Specific Populations (8.1)].

8.5 Geriatric Use

Of 401 patients treated with the recommended dosage regimen of NULOJIX, 15% were 65 years of age and older, while 3% were 75 and older. No overall differences in safety or effectiveness were observed between these subjects and younger subjects, but greater sensitivity or less efficacy in older individuals cannot be ruled out.

10 OVERDOSAGE

Single doses up to 20 mg per kg of NULOJIX have been administered to healthy subjects without apparent toxic effect. The administration of NULOJIX of higher cumulative dose and more frequent dosing than recommended in kidney transplant patients resulted in a higher frequency of CNS-related adverse reactions [see Adverse Reactions (6.1)]. In case of overdosage, it is recommended that the patient be monitored for any signs or symptoms of adverse reactions and appropriate symptomatic treatment instituted.

11 DESCRIPTION

NULOJIX® (belatacept), a selective T cell costimulation blocker, is a soluble fusion protein consisting of the modified extracellular domain of CTLA-4 fused to a portion (hinge-CH2-CH3 domains) of the Fc domain of a human immunoglobulin G1 antibody. Belatacept is produced by recombinant DNA technology in a mammalian cell expression system. Two amino acid substitutions (L104 to E; A29 to Y) were made in the ligand binding region of CTLA-4. As a result of these modifications, belatacept binds CD80 and CD86 more avidly than abatacept, the parent CTLA4-Immunoglobulin (CTLA4-Ig) molecule from which it is derived. The molecular weight of belatacept is approximately 90 kilodaltons.

NULOJIX is supplied as a sterile, white or off-white lyophilized powder for intravenous administration. Prior to use, the lyophile is reconstituted with a suitable fluid to obtain a clear to slightly opalescent, colorless to pale yellow solution, with a pH in the range of 7.2 to 7.8. Suitable fluids for constitution of the lyophile include SWFI, 0.9% NS, or D5W [see Dosage and Administration (2.2)]. Each 250 mg single-use vial of NULOJIX also contains: monobasic sodium phosphate (34.5 mg), sodium chloride (5.8 mg), and sucrose (500 mg).

12 CLINICAL PHARMACOLOGY

12.1 Mechanism of Action

Belatacept, a selective T cell (lymphocyte) costimulation blocker, binds to CD80 and CD86 on antigen-presenting cells thereby blocking CD28 mediated costimulation of T lymphocytes. In vitro, belatacept inhibits T lymphocyte proliferation and the production of the cytokines interleukin-2, interferon-γ, interleukin-4, and TNF-α. Activated T lymphocytes are the predominant mediators of immunologic rejection.

In non-human primate models of renal transplantation, belatacept monotherapy prolonged graft survival and decreased the production of anti-donor antibodies, compared to vehicle.

12.2 Pharmacodynamics

Belatacept-mediated costimulation blockade results in the inhibition of cytokine production by T cells required for antigen-specific antibody production by B cells. In clinical trials, greater reductions in mean immunoglobulin (IgG, IgM, and IgA) concentrations were observed from baseline to Month 6 and Month 12 post-transplant in belatacept-treated patients compared to cyclosporine-treated patients. In an exploratory subset analysis, a trend of decreasing IgG concentrations with increasing belatacept trough concentrations was observed at Month 6. Also in this exploratory subset analysis, belatacept-treated patients with CNS PTLD, CNS infections including PML, other serious infections, and malignancies were observed to have a higher incidence of IgG concentrations below the lower limit of the normal range (<694 mg/dL) at Month 6 than those patients who did not experience these adverse events. This observation was more pronounced with the higher than recommended dose of belatacept. A similar trend was also observed for cyclosporine-treated patients with serious infections and malignancies.

However, it is unclear whether any causal relationship between an IgG concentration below the lower level of normal and these adverse events exists, as the analysis may have been confounded by other factors (eg, age greater than 60 years, receipt of an extended criteria donor kidney, exposure to lymphocyte-depleting agents) which were also associated with IgG below the lower level of normal at Month 6 in these trials.

12.3 Pharmacokinetics

Table 5 summarizes the pharmacokinetic parameters of belatacept in healthy adult subjects after a single 10 mg per kg intravenous infusion; and in kidney transplant patients after the 10 mg per kg intravenous infusion at Week 12, and after 5 mg per kg intravenous infusion every four weeks at Month 12 post-transplant or later.

Table 5: Pharmacokinetic Parameters (Mean±SD [Range]) of Belatacept in Healthy Subjects and Kidney Transplant Patients After 5 and 10 mg per kg Intravenous Infusions Administered Over 30 Minutes
Pharmacokinetic Parameter | Healthy Subjects (After 10 mg per kg Single Dose) N=15 | Kidney Transplant Patients (After 10 mg per kg Multiple Doses) N=10 | Kidney Transplant Patients (After 5 mg per kg Multiple Doses) N=14
Peak concentration (Cmax) [µg/mL] | 300±77 (190-492) | 247±68 (161-340) | 139±28 (80-176)
AUCa [μg•h/mL] | 26398±5175 (18964-40684) | 22252±7868 (13575-42144) | 14090±3860 (7906-20510)
Terminal half-life (t1/2) [days] | 9.8±2.8 (6.4-15.6) | 9.8±3.2 (6.1-15.1) | 8.2±2.4 (3.1-11.9)
Systemic clearance (CL) [mL/h/kg] | 0.39±0.07 (0.25-0.53) | 0.49±0.13 (0.23-0.70) | 0.51±0.14 (0.33-0.75)
Volume of distribution (Vss) [L/kg] | 0.09±0.02 (0.07-0.15) | 0.11±0.03 (0.067-0.17) | 0.12±0.03 (0.09-0.17)
a AUC=AUC (INF) after single dose and AUC (TAU) after multiple dose, where TAU=4 weeks

In healthy subjects, the pharmacokinetics of belatacept was linear and the exposure to belatacept increased proportionally after a single intravenous infusion dose of 1 to 20 mg per kg. The pharmacokinetics of belatacept in de novo kidney transplant patients and healthy subjects are comparable. Following the recommended regimen, the mean belatacept serum concentration reached steady-state by Week 8 in the initial phase following transplantation and by Month 6 during the maintenance phase. Following once monthly intravenous infusion of 10 mg per kg and 5 mg per kg, there was about 20% and 10% systemic accumulation of belatacept in kidney transplant patients, respectively.

Based on population pharmacokinetic analysis of 924 kidney transplant patients up to one year post-transplant, the pharmacokinetics of belatacept were similar at different time periods post-transplant. In clinical trials, trough concentrations of belatacept were consistently maintained from Month 6 up to three years post-transplant. Population pharmacokinetic analyses in kidney transplant patients revealed that there was a trend toward higher clearance of belatacept with increasing body weight. Age, gender, race, renal function (measured by calculated glomerular filtration rate [GFR]), hepatic function (measured by albumin), diabetes, and concomitant dialysis did not affect the clearance of belatacept.

Drug Interactions

Mycophenolate Mofetil

In a pharmacokinetic substudy of Studies 1 and 2, the plasma concentrations of MPA were measured in 41 patients who received fixed MMF doses of 500 to 1500 mg twice daily with either 5 mg per kg of NULOJIX or cyclosporine. The mean dose-normalized MPA Cmax and AUC0-12 were approximately 20% and 40% higher, respectively, with NULOJIX coadministration than with cyclosporine coadministration [see Drug Interactions (7.1)].

Cytochrome P450 Substrates

The potential of NULOJIX to alter the systemic concentrations of drugs that are CYP450 substrates was investigated in healthy subjects following administration of a cocktail of probe drugs given concomitantly with, and at three days and at seven days following a single intravenous 10 mg per kg dose of NULOJIX. NULOJIX did not alter the pharmacokinetics of drugs that are substrates of CYP1A2 (caffeine), CYP2C9 (losartan), CYP2D6 (dextromethorphan), CYP3A (midazolam), and CYP2C19 (omeprazole) [see Drug Interactions (7.2)].

13 NONCLINICAL TOXICOLOGY

13.1 Carcinogenesis, Mutagenesis, Impairment of Fertility

A carcinogenicity study was not conducted with belatacept. However, a murine carcinogenicity study was conducted with abatacept (a more active analog in rodents) to determine the carcinogenic potential of CD28 blockade. Weekly subcutaneous injections of 20, 65, or 200 mg per kg of abatacept were associated with increases in the incidence of malignant lymphomas (all doses) and mammary gland tumors (intermediate- and high-dose in females) at clinically relevant exposures. The mice in this study were infected with endogenous murine leukemia and mouse mammary tumor viruses which are associated with an increased incidence of lymphomas and mammary gland tumors, respectively, in immunosuppressed mice. Although the precise relevance of these findings to the clinical use of NULOJIX is unknown, cases of PTLD (a premalignant or malignant proliferation of B lymphocytes) were reported in clinical trials.

Genotoxicity testing is not required for protein therapeutics; therefore, no genotoxicity studies were conducted with belatacept.

Belatacept had no adverse effects on male or female fertility in rats at doses up to 200 mg per kg daily (25 times the MRHD exposure).

13.2 Animal Toxicology and/or Pharmacology

Abatacept, a fusion protein that differs from belatacept by two amino acids, binds to the same ligands (CD80/CD86) and blocks T cell costimulation like belatacept, but is more active than belatacept in rodents. Therefore, toxicities identified with abatacept in rodents may be predictive of adverse effects in humans treated with belatacept.

Studies in rats exposed to abatacept have shown immune system abnormalities including a low incidence of infections leading to death (observed in juvenile rats and pregnant rats), as well as autoimmunity of the thyroid and pancreas (observed in rats exposed in utero, as juveniles or as adults). Studies of abatacept in adult mice and monkeys, as well as belatacept in adult monkeys, have not demonstrated similar findings.

The increased susceptibility to opportunistic infections observed in juvenile rats is likely associated with the exposure to abatacept before the complete development of memory immune responses. In pregnant rats, the increased susceptibility to opportunistic infections may be due to the inherent lapses in immunity that occur in rats during late pregnancy/lactation. Infections related to NULOJIX have been observed in human clinical trials [see Warnings and Precautions (5.5)].

Administration of abatacept to rats was associated with a significant decrease in T regulatory cells (up to 90%). Deficiency of T regulatory cells in humans has been associated with autoimmunity. The occurrence of autoimmune events across the core clinical trials was infrequent. However, the possibility that patients administered NULOJIX could develop autoimmunity (or that fetuses exposed to NULOJIX in utero could develop autoimmunity) cannot be excluded.

In a 6-month toxicity study with belatacept in cynomolgus monkeys administered weekly doses up to 50 mg per kg (6 times the MRHD exposure) and in a 1-year toxicity study with abatacept in adult cynomolgus monkeys administered weekly doses up to 50 mg per kg, no significant drug-related toxicities were observed. Reversible pharmacological effects consisted of minimal transient decreases in serum IgG and minimal to severe lymphoid depletion of germinal centers in the spleen and/or lymph nodes.

Following 5 doses (10 mg per kg or 50 mg per kg, once a week for five weeks) of systemic administration, belatacept was not detected in brain tissue of normal healthy cynomolgus monkeys. The number of cells expressing major histocompatibility complex (MHC) class-II antigens (potential marker of immune cell activation) in the brain were increased in monkeys administered belatacept compared to vehicle control. However, distribution of some other cells expressing CD68, CD20, CD80, and CD86, typically expressed on MHC class II-positive cells, was not altered and there were no other histological changes in the brain. The clinical relevance of the findings is unknown.

14 CLINICAL STUDIES

14.1 Prevention of Organ Rejection in Kidney Transplant Recipients

The efficacy and safety of NULOJIX in de novo kidney transplantation were assessed in two open-label, randomized, multicenter, active-controlled trials (Study 1 and Study 2). These trials evaluated two dose regimens of NULOJIX, the recommended dosage regimen [see Dosage and Administration (2.1)] and a regimen with higher cumulative doses and more frequent dosing than the recommended dosage regimen, compared to a cyclosporine control regimen. All treatment groups also received basiliximab induction, mycophenolate mofetil (MMF), and corticosteroids.

Treatment Regimen

The NULOJIX recommended regimen consisted of a 10 mg per kg dose administered on Day 1 (the day of transplantation, prior to implantation), Day 5 (approximately 96 hours after the Day 1 dose), end of Weeks 2 and 4; then every four weeks through Week 12 after transplantation. Starting at Week 16 after transplantation, NULOJIX was administered at the maintenance dose of 5 mg per kg every four weeks (plus or minus three days). NULOJIX was administered as an intravenous infusion over 30 minutes [see Dosage and Administration (2.1)].

Basiliximab 20 mg was administered intravenously on the day of transplantation and four days later.

The initial dose of MMF was 1 gram twice daily and was adjusted as needed, based on clinical signs of adverse events or efficacy failure.

The protocol-specified dosing of corticosteroids in Studies 1 and 2 at Day 1 was methylprednisolone (as sodium succinate) 500 mg IV on arrival in the operating room, Day 2, methylprednisolone 250 mg IV, and Day 3, prednisone 100 mg orally. Actual median corticosteroid doses used with the NULOJIX recommended regimen from Week 1 through Month 6 are summarized in the table below (Table 6).

Table 6: Actual Corticosteroida Dosing in Studies 1 and 2
Day of Dosing | Median (Q1–Q3) Daily Doseb,c
 | Study 1 | Study 2
Week 1 | 31.7 mg (26.7-50 mg) | 30 mg (26.7-50 mg)
Week 2 | 25 mg (20-30 mg) | 25 mg (20-30 mg)
Week 4 | 20 mg (15-20 mg) | 20 mg (15-22.5 mg)
Week 6 | 15 mg (10-20 mg) | 16.7 mg (12.5-20 mg)
Month 6 | 10 mg (5-10 mg) | 10 mg (5-12.5 mg)
a Corticosteroid = prednisone or prednisolone.
b The protocols allowed for flexibility in determining corticosteroid dose and rapidity of taper after Day 15. It is not possible to distinguish corticosteroid doses used to treat acute rejection versus doses used in a maintenance regimen.
c Q1 and Q3 are the 25th and 75th percentiles of daily corticosteroid doses, respectively.

Study 1 enrolled recipients of living donor and standard criteria deceased donor organs and Study 2 enrolled recipients of extended criteria donor organs. Standard criteria donor organs were defined as organs from a deceased donor with anticipated cold ischemia time of <24 hours and not meeting the definition of extended criteria donor organs. Extended criteria donors were defined as deceased donors with at least one of the following: (1) donor age ≥60 years; (2) donor age ≥50 years and other donor comorbidities (≥2 of the following: stroke, hypertension, serum creatinine >1.5 mg/dL); (3) donation of organ after cardiac death; or (4) anticipated cold ischemia time of the organ of ≥24 hours. Study 1 excluded recipients undergoing a first transplant whose current Panel Reactive Antibodies (PRA) were ≥50% and recipients undergoing a retransplantation whose current PRA were ≥30%; Study 2 excluded recipients with a current PRA ≥30%. Both studies excluded recipients with HIV, hepatitis C, or evidence of current hepatitis B infection; recipients with active tuberculosis; and recipients in whom intravenous access was difficult to obtain.

Efficacy data are presented for the NULOJIX recommended regimen and cyclosporine regimen in Studies 1 and 2.

The NULOJIX regimen with higher cumulative doses and more frequent dosing of belatacept was associated with more efficacy failures. Higher doses and/or more frequent dosing of NULOJIX are not recommended [see Dosage and Administration (2.1), Warnings and Precautions (5.1), and Adverse Reactions (6.1)].

Study 1: Recipients of Living Donor and Standard Criteria Deceased Donor Kidneys

In Study 1 (NCT00256750), 666 patients were enrolled, randomized, and transplanted: 226 to the NULOJIX recommended regimen, 219 to the NULOJIX regimen with higher cumulative doses and more frequent dosing than recommended, and 221 to cyclosporine control regimen. The median age was 45 years; 58% of organs were from living donors; 3% were re-transplanted; 69% of the study population was male; 61% of patients were white, 8% were black/African-American, 31% were categorized as of other races; 16% had PRA ≥10%; 41% had 4 to 6 HLA mismatches; and 27% had diabetes prior to transplant. The incidence of delayed graft function was similar in all treatment arms (14% to 18%).

Premature discontinuation from treatment at the end of the first year occurred in 19% of patients receiving the NULOJIX recommended regimen and 19% of patients on the cyclosporine regimen. Among the patients who received the NULOJIX recommended regimen, 10% discontinued due to lack of efficacy, 5% due to adverse events, and 4% for other reasons. Among the patients who received the cyclosporine regimen, 9% discontinued due to adverse events, 5% due to lack of efficacy, and 5% for other reasons.

At the end of three years, 25% of patients receiving the NULOJIX recommended regimen and 34% of patients receiving the cyclosporine regimen had discontinued from treatment. Among the patients who received the NULOJIX recommended regimen, 12% discontinued due to lack of efficacy, 7% due to adverse events, and 6% for other reasons. Among the patients who received the cyclosporine regimen, 15% discontinued due to adverse events, 8% due to lack of efficacy, and 11% for other reasons.

Assessment of Efficacy

Table 7 summarizes the results of Study 1 following one and three years of treatment with the NULOJIX recommended dosage regimen and the cyclosporine control regimen. Efficacy failure at one year was defined as the occurrence of biopsy proven acute rejection (BPAR), graft loss, death, or lost to follow-up. BPAR was defined as histologically confirmed acute rejection by a central pathologist on a biopsy done for any reason, whether or not accompanied by clinical signs of rejection. Patient and graft survival was also assessed separately.

Table 7: Efficacy Outcomes by Years 1 and 3 for Study 1: Recipients of Living and Standard Criteria Deceased Donor Kidneys
Parameter | NULOJIX Recommended Regimen N=226 n (%) | Cyclosporine (CSA) N=221 n (%) | NULOJIX-CSA (97.3% CI)
Efficacy Failure by Year 1 | 49 (21.7) | 37 (16.7) | 4.9 (−3.3, 13.2)
Components of Efficacy Failurea
Biopsy Proven Acute Rejection | 45 (19.9) | 23 (10.4)
Graft Loss | 5 (2.2) | 8 (3.6)
Death | 4 (1.8) | 7 (3.2)
Lost to follow-up | 0 | 1 (0.5)
Efficacy Failure by Year 3 | 58 (25.7) | 57 (25.8) | −0.1 (−9.3, 9)
Components of Efficacy Failurea
Biopsy Proven Acute Rejection | 50 (22.1) | 31 (14)
Graft Loss | 9 (4) | 10 (4.5)
Death | 10 (4.4) | 15 (6.8)
Lost to follow-up | 2 (0.9) | 5 (2.3)
Patient and graft survivalb
Year 1 | 218 (96.5) | 206 (93.2) | 3.2 (−1.5, 8.4)
Year 3 | 206 (91.2) | 192 (86.9) | 4.3 (−2.2, 10.8)
a Patients may have experienced more than one event.
b Patients known to be alive with a functioning graft.

In Study 1, the rate of BPAR at one year and three years was higher in patients treated with the NULOJIX recommended regimen than the cyclosporine regimen. Of the patients who experienced BPAR with NULOJIX, 70% experienced BPAR by Month 3, and 84% experienced BPAR by Month 6. By three years, recurrent BPAR occurred with similar frequency across treatment groups (<3%). The component of BPAR determined by biopsy only (subclinical protocol-defined acute rejection) was 5% in both treatment groups.

Patients treated with the NULOJIX recommended regimen experienced episodes of BPAR classified as Banff grade IIb or higher (6% [14/226] at one year and 7% [15/226] at three years) more frequently compared to patients treated with the cyclosporine regimen (2% [4/221] at one year and 2% [5/221] at three years). Also, T cell-depleting therapy was used more frequently to treat episodes of BPAR in NULOJIX-treated patients (10%; 23/226) compared to cyclosporine-treated patients (2%; 5/221). At Month 12, the difference in mean calculated glomerular filtration rate (GFR) between patients with and without history of BPAR was 19 mL/min/1.73 m^2 among NULOJIX-treated patients compared to 7 mL/min/1.73 m^2 among cyclosporine-treated patients. By three years, 22% (11/50) of NULOJIX-treated patients with a history of BPAR experienced graft loss and/or death compared to 10% (3/31) of cyclosporine-treated patients with a history of BPAR; at that time point, 10% (5/50) of NULOJIX-treated patients experienced graft loss and 12% (6/50) of NULOJIX-treated patients had died following an episode of BPAR, whereas 7% (2/31) of cyclosporine-treated patients experienced graft loss and 7% (2/31) of cyclosporine-treated patients had died following an episode of BPAR. The overall prevalence of donor-specific antibodies was 5% and 11% for the NULOJIX recommended regimen and cyclosporine, respectively, up to 36 months post-transplant.

While the difference in GFR in patients with BPAR versus those without BPAR was greater in patients treated with NULOJIX than cyclosporine, the mean GFR following BPAR was similar in NULOJIX (49 mL/min/1.73 m^2) and cyclosporine treated patients (43 mL/min/1.73 m^2) at one year. The relationship between BPAR, GFR, and patient and graft survival is unclear due to the limited number of patients who experienced BPAR, differences in renal hemodynamics (and, consequently, GFR) across maintenance immunosuppression regimens, and the high rate of switching treatment regimens after BPAR.

Assessment of Efficacy in the EBV Seropositive Subpopulation

NULOJIX is recommended for use only in EBV seropositive patients [see Indications and Usage (1.2)].

In Study 1, approximately 87% of patients were EBV seropositive prior to transplant. Efficacy results in the EBV seropositive subpopulation were consistent with those in the total population studied.

By one year, the efficacy failure rate in the EBV seropositive population was 21% (42/202) in patients treated with the NULOJIX recommended regimen and 17% (31/184) in patients treated with cyclosporine (difference=4%, 97.3% CI [−4.8, 12.8]). Patient and graft survival was 98% (198/202) in NULOJIX-treated patients and 92% (170/184) in cyclosporine-treated patients (difference=5.6%, 97.3% CI [0.8, 10.4]).

By three years, efficacy failure was 25% in both treatment groups and patient and graft survival was 94% (187/202) in NULOJIX-treated patients compared with 88% (162/184) in cyclosporine-treated patients (difference=4.6%, 97.3% CI [−2.1, 11.3]).

Assessment of Glomerular Filtration Rate (GFR)

Glomerular Filtration Rate (GFR) was measured at one and two years and was calculated using the Modification of Diet in Renal Disease (MDRD) formula at one, two, and three years after transplantation. As shown in Table 8, both measured and calculated GFR was higher in patients treated with the NULOJIX recommended regimen compared to patients treated with the cyclosporine control regimen at all time points. As shown in Figure 1, the differences in GFR were apparent in the first month after transplant and were maintained up to three years (36 months). An analysis of change of calculated mean GFR between three and 36 months demonstrated an increase of 0.8 mL/min/year (95% CI [−0.2, 1.8]) for NULOJIX-treated patients and a decrease of 2.2 mL/min/year (95% CI [−3.2, −1.2]) for cyclosporine-treated patients.

Table 8: Measured and Calculated GFR for Study 1: Recipients of Living and Standard Criteria Deceased Donor Kidneys
Parameter | NULOJIX Recommended Regimen N=226 | Cyclosporine (CSA) N=221 | NULOJIX-CSA (97.3% CI)
Measured GFRa mL/min/1.73 m^2 mean (SD)
Year 1 | 63.4 (27.7) | 50.4 (18.7) | 13.0 (7.3, 18.7)
 | (n=206) | (n=199)
Year 2b | 67.9 (29.9) | 50.5 (20.5) | 17.4 (11.5, 23.4)
 | (n=199) | (n=185)
Calculated GFRc mL/min/1.73 m^2 mean (SD)
Year 1 | 65.4 (22.9) | 50.1 (21.1) | 15.3 (10.3, 20.3)
 | (n=200) | (n=199)
Year 2 | 65.4 (25.2) | 47.9 (23) | 17.5 (12, 23.1)
 | (n=201) | (n=182)
Year 3 | 65.8 (27) | 44.4 (23.6) | 21.4 (15.4, 27.4)
 | (n=190) | (n=171)
a GFR was measured using the cold-iothalamate method.
b Measured GFR was not assessed at Year 3.
c GFR was calculated using the MDRD formula.

Figure 1: Calculated (MDRD) GFR Through Month 36; Study 1: Recipients of Living and Standard Criteria Deceased Donor Kidneys

Assessment of Chronic Allograft Nephropathy (CAN)

The prevalence of chronic allograft nephropathy (CAN) at one year, as defined by the Banff ’97 classification system, was 24% (54/226) in patients treated with the NULOJIX recommended regimen and in 32% (71/219) of patients treated with the cyclosporine control regimen. CAN was not evaluated after the first year following transplantation. The clinical significance of this finding is unknown.

Study 2: Recipients of Extended Criteria Donor Kidneys

In Study 2 (NCT00114777), 543 patients were enrolled, randomized, and transplanted: 175 to the NULOJIX recommended regimen, 184 to the NULOJIX regimen with higher cumulative doses and more frequent dosing than recommended, and 184 to the cyclosporine control regimen. The median age was 58 years; 67% of the study population was male; 75% of patients were white, 13% were black/African-American, 12% were categorized as of other races; 3% had PRA ≥10%; 53% had 4 to 6 HLA mismatches; and 29% had diabetes prior to transplantation. The incidence of delayed graft function was similar in all treatment arms (47% to 49%).

Premature discontinuation from treatment at the end of the first year occurred in 25% of patients receiving the NULOJIX recommended regimen and 30% of patients receiving the cyclosporine control regimen. Among the patients who received the NULOJIX recommended regimen, 14% discontinued due to adverse events, 9% due to lack of efficacy, and 2% for other reasons. Among the patients who received the cyclosporine regimen, 17% discontinued due to adverse events, 7% due to lack of efficacy, and 6% for other reasons.

At the end of three years, 35% of patients receiving the NULOJIX recommended regimen and 44% of patients receiving the cyclosporine regimen had discontinued from treatment. Among the patients who received the NULOJIX recommended regimen, 20% discontinued due to adverse events, 9% due to lack of efficacy, and 6% for other reasons. Among the patients who received the cyclosporine regimen, 25% discontinued due to adverse events, 10% due to lack of efficacy, and 10% for other reasons.

Assessment of Efficacy

Table 9 summarizes the results of Study 2 following one and three years of treatment with the NULOJIX recommended dosage regimen and the cyclosporine control regimen. Efficacy failure at one year was defined as the occurrence of biopsy proven acute rejection (BPAR), graft loss, death, or lost to follow-up. BPAR was defined as histologically confirmed acute rejection by a central pathologist on a biopsy done for any reason, whether or not accompanied by clinical signs of rejection. Patient and graft survival was also assessed.

Table 9: Efficacy Outcomes by Years 1 and 3 for Study 2: Recipients of Extended Criteria Donor Kidneys
Parameter | NULOJIX Recommended Regimen N=175 n (%) | Cyclosporine (CSA) N=184 n (%) | NULOJIX-CSA (97.3% CI)
Efficacy Failure by Year 1 | 51 (29.1) | 52 (28.3) | 0.9 (−9.7, 11.5)
Components of Efficacy Failurea
Biopsy Proven Acute Rejection | 37 (21.1) | 34 (18.5)
Graft Loss | 16 (9.1) | 20 (10.9)
Death | 5 (2.9) | 8 (4.3)
Lost to follow-up | 0 | 2 (1.1)
Efficacy Failure by Year 3 | 63 (36) | 68 (37) | −1.0 (−12.1, 10.3)
Components of Efficacy Failurea
Biopsy Proven Acute Rejection | 42 (24) | 42 (22.8)
Graft Loss | 21 (12) | 23 (12.5)
Death | 15 (8.6) | 17 (9.2)
Lost to follow-up | 1 (0.6) | 5 (2.7)
Patient and graft survivalb
Year 1 | 155 (88.6) | 157 (85.3) | 3.2 (−4.8, 11.3)
Year 3 | 143 (81.7) | 143 (77.7) | 4.0 (−5.4, 13.4)
a Patients may have experienced more than one event.
b Patients known to be alive with a functioning graft.

In Study 2, the rate of BPAR at one year and three years was similar in patients treated with NULOJIX and cyclosporine. Of the patients who experienced BPAR with NULOJIX, 62% experienced BPAR by Month 3, and 76% experienced BPAR by Month 6. By three years, recurrent BPAR occurred with similar frequency across treatment groups (<3%). The component of BPAR determined by biopsy only (subclinical protocol-defined acute rejection) was 5% in both treatment groups.

A similar proportion of patients in the NULOJIX recommended regimen group experienced BPAR classified as Banff grade IIb or higher (5% [9/175] at one year and 6% [10/175] at three years) compared to patients treated with the cyclosporine regimen (4% [7/184] at one year and 5% [9/184] at three years). Also, T cell-depleting therapy was used with similar frequency to treat any episode of BPAR in NULOJIX-treated patients (5% or 9/175) compared to cyclosporine-treated patients (4% or 7/184). At Month 12, the difference in mean calculated GFR between patients with and without a history of BPAR was 10 mL/min/1.73 m^2 among NULOJIX-treated patients compared to 14 mL/min/1.73 m^2 among cyclosporine-treated patients. By three years, 24% (10/42) of NULOJIX-treated patients with a history of BPAR experienced graft loss and/or death compared to 31% (13/42) of cyclosporine-treated patients with a history of BPAR; at that time point, 17% (7/42) of NULOJIX-treated patients experienced graft loss and 14% (6/42) of NULOJIX-treated patients had died following an episode of BPAR, whereas 19% (8/42) of cyclosporine-treated patients experienced graft loss and 19% (8/42) of cyclosporine-treated patients had died following an episode of BPAR. The overall prevalence of donor-specific antibodies was 6% and 15% for the NULOJIX recommended regimen and cyclosporine, respectively, up to 36 months post-transplant.

The mean GFR following BPAR was 36 mL/min/1.73 m^2 in NULOJIX patients and 24 mL/min/1.73 m^2 in cyclosporine-treated patients at one year. The relationship between BPAR, GFR, and patient and graft survival is unclear due to the limited number of patients who experienced BPAR, differences in renal hemodynamics (and, consequently, GFR) across maintenance immunosuppression regimens, and the high rate of switching treatment regimens after BPAR.

Assessment of Efficacy in the EBV Seropositive Subpopulation

NULOJIX is recommended for use only in EBV seropositive patients [see Indications and Usage (1.2)].

In Study 2, approximately 91% of the patients were EBV seropositive prior to transplant. Efficacy results in the EBV seropositive subpopulation were consistent with those in the total population studied.

By one year, the efficacy failure rate in the EBV seropositive population was 29% (45/156) in patients treated with the NULOJIX recommended regimen and 28% (47/168) in patients treated with cyclosporine (difference=0.8%, 97.3% CI [−10.3, 11.9]). Patient and graft survival rate in the EBV seropositive population was 89% (139/156) in the NULOJIX-treated patients and 86% (144/168) in cyclosporine-treated patients (difference=3.4%, 97.3% CI [−4.7, 11.5]).

By three years, efficacy failure was 35% (54/156) in NULOJIX-treated patients and 36% (61/168) in cyclosporine-treated patients. Patient and graft survival was 83% (130/156) in NULOJIX-treated patients compared with 77% (130/168) in cyclosporine-treated patients (difference=5.9%, 97.3% CI [−3.8, 15.6]).

Assessment of Glomerular Filtration Rate (GFR)

Glomerular Filtration Rate (GFR) was measured at one and two years and was calculated using the Modification of Diet in Renal Disease (MDRD) formula at one, two, and three years after transplantation. As shown in Table 10, both measured and calculated GFR was higher in patients treated with the NULOJIX recommended regimen compared to patients treated with the cyclosporine control regimen at all time points. As shown in Figure 2, the differences in GFR were apparent in the first month after transplant and were maintained up to three years (36 months). An analysis of change of calculated mean GFR between Month 3 and Month 36 demonstrated a decrease of 0.8 mL/min/year (95% CI [−1.9, 0.3]) for NULOJIX-treated patients and a decrease of 2.0 mL/min/year (95% CI [−3.1, −0.8]) for cyclosporine-treated patients.

Table 10: Measured and Calculated GFR for Study 2: Recipients of Extended Criteria Donor Kidneys
Parameter | NULOJIX Recommended Regimen N=175 | Cyclosporine (CSA) N=184 | NULOJIX-CSA (97.3% CI)
Measured GFRa mL/min/1.73 m^2 mean (SD)
Year 1 | 49.6 (25.8) | 45.2 (21.1) | 4.3 (−1.5, 10.2)
 | (n=151) | (n=154)
Year 2b | 49.7 (23.7) | 45.0 (27.2) | 4.7 (−1.8, 11.3)
 | (n=139) | (n=136)
Calculated GFRc mL/min/1.73 m^2 mean (SD)
Year 1 | 44.5 (21.8) | 36.5 (21.1) | 8.0 (2.5, 13.4)
 | (n=158) | (n=159)
Year 2 | 42.8 (24.1) | 34.9 (21.6) | 8.0 (1.9, 14)
 | (n=158) | (n=154)
Year 3 | 42.2 (25.2) | 31.5 (22.1) | 10.7 (4.3, 17.2)
 | (n=154) | (n=143)
a GFR was measured using the cold-iothalamate method.
b Measured GFR was not assessed at Year 3.
c GFR was calculated using the MDRD formula.

Figure 2: Calculated (MDRD) GFR Through Month 36; Study 2: Recipients of Extended Criteria Donor Kidneys

Assessment of Chronic Allograft Nephropathy (CAN)

The prevalence of chronic allograft nephropathy (CAN) at one year, as defined by the Banff ’97 classification system, was 46% (80/174) in patients treated with the NULOJIX recommended regimen and 52% (95/184) of patients treated with the cyclosporine control regimen. CAN was not evaluated after the first year following transplantation. The clinical significance of this finding is unknown.

14.2 Long-Term Extension (LTE) of Study 1 and Study 2

Although initially designed as three-year studies, Studies 1 and 2 were subsequently extended to seven years to provide descriptive long-term safety and efficacy data. Only patients who completed the assigned treatment for three years and consented to remain on the assigned treatment from three to seven years were eligible for the long-term extension (LTE) studies.

Long-Term Extension of Study 1

In the LTE of Study 1, of the 666 originally randomized and transplanted patients, 457 (69%) patients enrolled into the LTE study: 73% (166/226) in the NULOJIX recommended regimen group, 71% (155/219) in the NULOJIX nonrecommended regimen group, and 62% (136/221) in the cyclosporine group. Fourteen (2%) patients who completed the assigned treatment at the end of Year 3 did not enroll into the LTE study: 4 in the NULOJIX recommended regimen group, 3 in the NULOJIX nonrecommended regimen group, and 7 in the cyclosporine group.

Of the 457 patients enrolled in the LTE study, 356 (79%) patients completed the assigned treatment at the end of Year 7: 82% (136/166) in the NULOJIX recommended regimen group, 83% (128/155) in the NULOJIX nonrecommended regimen group, and 68% (92/136) in the cyclosporine group. The most common reasons for discontinuation from the LTE study included adverse events and death.

Seven (4.2%) deaths and 2 (1.2%) graft losses were reported in the NULOJIX recommended regimen group while 7 (4.5%) deaths and no graft loss were reported in the NULOJIX nonrecommended regimen group, and 10 (7.4%) deaths and 6 (4.4%) graft losses were reported in the cyclosporine group.

No PTLD was reported in the NULOJIX groups while 1 case of non-CNS PTLD was reported in the cyclosporine group, in a patient who was EBV seropositive at the time of transplant.

No PML was reported in the NULOJIX groups while 1 case of PML was reported in the cyclosporine group at 82 months post-transplant (56 days after discontinuing therapy).

The higher calculated GFR observed in NULOJIX-treated patients compared to cyclosporine-treated patients during the first three years was maintained during the LTE period.

Table 11: Events Reported in Long-Term Extension from 36 to 84 Months Post-Transplant of Study 1: Recipients of Living and Standard Criteria Deceased Donor Kidneys
 | NULOJIX Recommended Regimen N=166 n (%) | NULOJIX Nonrecommended Regimen N=155 n (%) | Cyclosporine N=136 n (%)
Death | 7 (4.2) | 7 (4.5) | 10 (7.4)
Graft Loss | 2 (1.2) | 0 (0) | 6 (4.4)
Death or Graft Loss | 9 (5.4) | 7 (4.5) | 14 (10.3)
PTLD | 0 (0) | 0 (0) | 1a (0.7)
PML | 0 (0) | 0 (0) | 1 (0.7)
a This patient was EBV seropositive at the time of transplant.

Long-Term Extension of Study 2

In the LTE of Study 2, of the 543 originally randomized and transplanted patients, 304 (56%) patients enrolled into the LTE study: 65% (113/175) in the NULOJIX recommended regimen group, 57% (104/184) in the NULOJIX nonrecommended regimen group, and 47% (87/184) in the cyclosporine group. Nineteen (3.5%) patients who completed the assigned treatment at the end of Year 3 did not enroll into the LTE study: 1 in the NULOJIX recommended regimen group, 5 in the NULOJIX nonrecommended regimen group, and 13 in the cyclosporine group.

Of the 304 patients enrolled in the LTE study, 215 (71%) patients completed the assigned treatment at the end of Year 7: 74% (84/113) in the NULOJIX recommended regimen group, 71% (74/104) in the NULOJIX nonrecommended regimen group, and 66% (57/87) in the cyclosporine group. The most common reasons for discontinuation from the LTE study included adverse events and death.

Twenty-one (18.6%) deaths and 1 (0.9%) graft loss were reported in the NULOJIX recommended regimen group while 14 (13.5%) deaths and 2 (1.9%) graft losses were reported in the NULOJIX nonrecommended regimen group, and 9 (10.3%) deaths and 6 (6.9%) graft losses were reported in the cyclosporine group.

Six cases of PTLD were reported among the three treatment groups: 4 in the NULOJIX recommended regimen group, 1 in the NULOJIX nonrecommended regimen group, and 1 in the cyclosporine group. Three of these cases (1 in each treatment group) occurred in patients who were EBV seropositive at the time of transplant and the other 3 cases (in NULOJIX recommended regimen) occurred in patients who were EBV seronegative. No case of PML was reported among the three treatment groups.

The higher mean calculated GFR observed in NULOJIX-treated patients compared to cyclosporine-treated patients during the first three years was maintained during the LTE period.

Table 12: Events Reported in Long-Term Extension from 36 to 84 Months Post-Transplant of Study 2: Recipients of Extended Criteria Donor Kidneys
 | NULOJIX Recommended Regimen N=113 n (%) | NULOJIX Nonrecommended Regimen N=104 n (%) | Cyclosporine N=87 n (%)
Death | 21 (18.6) | 14 (13.5) | 9 (10.3)
Graft Loss | 1 (0.9) | 2 (1.9) | 6 (6.9)
Death or Graft Loss | 22 (19.5) | 16 (15.4) | 14 (16.1)
PTLD | 4a (3.6) | 1 (1.0) | 1 (1.2)
PML | 0 (0) | 0 (0) | 0 (0)
a Three of these patients were EBV seronegative at the time of transplant.

14.3 Follow-Up Data of Patients with Complete 7-Year Patient and Graft Survival

In Study 1, of the original intention-to-treat (ITT) population (N=666), 72% (163/226) of patients in the NULOJIX recommended regimen group, 70% (153/219) of patients in the NULOJIX nonrecommended regimen group and 60% (132/221) of patients in the cyclosporine group had complete 7-year patient and graft survival follow-up data. Among these completers, the proportion of patients who died or had graft loss was 17% (27/163) in the NULOJIX recommended regimen group, 16% (25/153) in the NULOJIX nonrecommended regimen group and 30% (40/132) in the cyclosporine group.

In Study 2, of the original ITT population (N=543), 79% (138/175) of patients in the NULOJIX recommended regimen group, 128/184 (70%) of patients in the NULOJIX nonrecommended regimen group and 59% (108/184) of patients in the cyclosporine group had complete 7-year patient and graft survival follow-up data. Among these completers, the proportion of patients who died or had graft loss was 39% (54/138) in the NULOJIX recommended regimen group, 42% (54/128) in the NULOJIX nonrecommended regimen group and 48% (52/108) in the cyclosporine group.

Table 13: Events Reported in Patients with Complete 7-Year Patient and Graft Survival Follow-Up Data
 | NULOJIX Recommended Regimen n (%) | NULOJIX Nonrecommended Regimen n (%) | Cyclosporine n (%)
Study 1 | N=163 | N=153 | N=132
Death | 17 (10%) | 17 (11%) | 26 (20%)
Graft Loss | 11 (7%) | 10 (7%) | 17 (13%)
Death or Graft Loss | 27 (17%) | 25 (16%) | 40 (30%)
Study 2 | N=138 | N=128 | N=108
Death | 37 (27%) | 37 (29%) | 29 (27%)
Graft Loss | 23 (17%) | 21 (16%) | 29 (27%)
Death or Graft Loss | 54 (39%) | 54 (42%) | 52 (48%)

16 HOW SUPPLIED/STORAGE AND HANDLING

NULOJIX® (belatacept) lyophilized powder for intravenous infusion is supplied as a single-use vial with a silicone-free disposable syringe in the following packaging configuration:

Description |  | NDC Number
One 250-mg vial | One 12 mL Syringe | 0003-0371-13

16.1 Storage

NULOJIX lyophilized powder is stored refrigerated at 2°C to 8°C (36°F to 46°F). Protect NULOJIX from light by storing in the original package until time of use.

The reconstituted solution should be transferred from the vial to the infusion bag or bottle immediately. The NULOJIX infusion must be completed within 24 hours of constitution of the NULOJIX lyophilized powder. If not used immediately, the infusion solution may be stored under refrigeration conditions: 2°C to 8°C (36°F to 46°F) and protected from light for up to 24 hours (a maximum of 4 hours of the total 24 hours can be at room temperature: 20°C to 25°C [68°F to 77°F] and room light) [see Dosage and Administration (2.2)].

17 PATIENT COUNSELING INFORMATION

Advise the patient to read the FDA-approved patient labeling (Medication Guide).

Post-Transplant Lymphoproliferative Disorder

The overall risk of PTLD, especially CNS PTLD, was elevated in NULOJIX-treated patients. Instruct patients to immediately report any of the following neurological, cognitive, or behavioral signs and symptoms during and after therapy with NULOJIX [see Boxed Warning and Warnings and Precautions (5.1)]:

- changes in mood or usual behavior
- confusion, problems thinking, loss of memory
- changes in walking or talking
- decreased strength or weakness on one side of the body
- changes in vision

Other Malignancies

Inform patients about the increased risk of malignancies, in addition to PTLD, while taking immunosuppressive therapy, especially skin cancer. Instruct patients to limit exposure to sunlight and UV light by wearing protective clothing and using a sunscreen with a high protection factor. Instruct patients to look for any signs and symptoms of skin cancer, such as suspicious moles or lesions [see Warnings and Precautions (5.3)].

Progressive Multifocal Leukoencephalopathy

Cases of PML have been reported in NULOJIX-treated patients. Instruct patients to immediately report any of the following neurological, cognitive, or behavioral signs and symptoms during and after therapy with NULOJIX [see Warnings and Precautions (5.4)]:

- changes in mood or usual behavior
- confusion, problems thinking, loss of memory
- changes in walking or talking
- decreased strength or weakness on one side of the body
- changes in vision

Other Serious Infections

Inform patients about the increased risk of infection while taking immunosuppressive therapy. Instruct patients to adhere to antimicrobial prophylaxis regimens as prescribed. Tell patients to immediately report any signs and symptoms of infection during therapy with NULOJIX [see Warnings and Precautions (5.5)].

Immunizations

Inform patients that vaccinations may be less effective while they are being treated with NULOJIX. Advise patients that live vaccines should be avoided [see Warnings and Precautions (5.8)].

Pregnant Women and Nursing Mothers

Inform patients that NULOJIX has not been studied in pregnant women or nursing mothers so the effects of NULOJIX on pregnant women or nursing infants are not known. Instruct patients to tell their healthcare provider if they are pregnant, become pregnant, or are thinking about becoming pregnant [see Use in Specific Populations (8.1)]. Instruct patients to tell their healthcare provider if they plan to breast-feed their infant [see Use in Specific Populations (8.2)].

Bristol-Myers Squibb Company
Princeton, New Jersey 08543
U.S. License No. 1713

MEDICATION GUIDE NULOJIX® (noo-LOJ-jiks) (belatacept) For Injection, For Intravenous Use

Read this Medication Guide before you start receiving NULOJIX and before each treatment. There may be new information. This Medication Guide does not take the place of talking with your doctor about your medical condition or your treatment.

What is the most important information I should know about NULOJIX?

NULOJIX increases your risk of serious side effects, including:

- Post-transplant lymphoproliferative disorder (PTLD). PTLD is a condition that can happen if certain white blood cells grow out of control after an organ transplant because your immune system is weak. PTLD can get worse and become a type of cancer. PTLD can lead to death.
  People treated with NULOJIX have a higher risk of getting PTLD. If you get PTLD with NULOJIX you are at especially high risk of getting it in your brain. Your risk for PTLD is also higher if you:
  - have never been exposed to the Epstein-Barr virus (EBV). Your doctor should test you for EBV. Do not receive NULOJIX unless you are EBV positive (you have been exposed to EBV).
  - get an infection with a virus called cytomegalovirus (CMV).
  - receive treatment for transplant rejection that lowers certain white blood cells called T lymphocytes.
- Increased risk of getting cancers other than PTLD. People who take medicines that weaken the immune system, including NULOJIX, have a higher risk of getting other cancers, including skin cancer. Talk to your doctor about your risk for cancer. See "What should I avoid while receiving NULOJIX?"
- Progressive multifocal leukoencephalopathy (PML). PML is a rare, serious brain infection caused by JC virus. People with weakened immune systems are at risk for getting PML. PML can result in death or severe disability. There is no known prevention, treatment, or cure for PML.
- Increased risk of getting other serious infections, including tuberculosis (TB) and other infections caused by bacteria, viruses, or fungi. These serious infections may lead to death. Also, a virus called BK virus can affect how your kidney works and cause your transplanted kidney to fail.

Tell your doctor right away if you get any of the following symptoms during treatment with NULOJIX:

- change in mood or your usual behavior
- confusion or problems thinking or with memory
- change in the way you walk or talk
- decreased strength or weakness on one side of your body
- change in vision
- fever, night sweats, or tiredness that does not go away
- weight loss
- swollen glands
- flu, cold symptoms, or cough
- stomach-area pain
- vomiting or diarrhea
- tenderness over your transplanted kidney
- change in the amount of urine that you make, blood in your urine, pain or burning on urination
- a new skin lesion or bump, or change in size or color of a mole

See "What are the possible side effects of NULOJIX?" for more information about side effects.

Liver transplant patients should not receive NULOJIX because of an increased risk of losing the transplanted liver (graft loss) and death. Talk to your doctor if you would like more information about this risk.

What is NULOJIX?

NULOJIX is a prescription medicine used in adults to prevent transplant rejection in people who have received a kidney transplant. Transplant rejection happens when the body’s immune system senses that the new transplanted kidney is different or foreign, and attacks it. NULOJIX is used with corticosteroids and certain other medicines to help prevent rejection of your new kidney.

It is not known if NULOJIX is safe and effective in children under 18 years of age.

NULOJIX is only used in people who have been exposed to the EBV virus.

It is not known if NULOJIX is safe and effective in people who receive an organ transplant other than a kidney transplant.

Who should not receive NULOJIX?

Do not receive treatment with NULOJIX if you are EBV negative. Your doctor will do a test to see if you were exposed to EBV in the past.

What should I tell my doctor before receiving NULOJIX?

Before receiving NULOJIX, tell your doctor if you:

- plan to receive any vaccines. Talk to your doctor about which vaccines are safe for you to receive during your treatment with NULOJIX. See “What should I avoid while receiving NULOJIX?”
- have any other medical conditions
- are pregnant or plan to become pregnant. It is not known if NULOJIX will harm your unborn baby. If you become pregnant while taking NULOJIX:
  - Tell your doctor right away. You and your doctor should decide if you will keep receiving NULOJIX while you are pregnant.
  - Talk with your doctor about enrolling in the National Transplant Pregnancy Registry (NTPR). This Registry collects information about pregnancies in women who have received NULOJIX or if their partner has received NULOJIX, and had a transplant. You can also enroll by calling 1-877-955-6877.
- are breast-feeding or plan to breast-feed. It is not known if NULOJIX passes into your breast milk. You and your doctor should decide if you will receive NULOJIX or breast-feed. You should not do both.

Tell your doctor about all of the medicines you take, including prescription and non-prescription medicines, vitamins, and herbal supplements.

Know the medicines you take. Keep a list of them to show your doctor and pharmacist when you get a new medicine. Do not take any new medicine without talking with your transplant doctor first.

How will I receive NULOJIX?

- To help prevent rejection of your new kidney, you will receive NULOJIX regularly as prescribed by your doctor. It is important for you to keep all your appointments for NULOJIX treatment and follow up.
- You will receive NULOJIX as an intravenous (IV) infusion in your arm. Each IV infusion takes about 30 minutes.
- During treatment with NULOJIX, your doctor will test your blood and urine to check how your kidney is working.
- Take all the medicines prescribed by your doctor to prevent infection or transplant rejection. Take them exactly as your doctor tells you. Talk to your doctor or pharmacist if you have any questions about how to take your medicines.

What should I avoid while receiving NULOJIX?

- Limit the amount of time you spend in sunlight. Avoid using tanning beds or sunlamps. People who take medicines that weaken the immune system, including NULOJIX, have a higher risk of getting cancer, including skin cancer. Wear protective clothing and use sunscreen with a high protection factor (SPF) when you have to be in the sun.
- Avoid receiving live vaccines during treatment with NULOJIX. Talk to your doctor to find out which vaccines are safe for you during this time. Some vaccines may not work as well while you are receiving NULOJIX. See “What should I tell my doctor before receiving NULOJIX?”

What are the possible side effects of NULOJIX?

NULOJIX increases your risk of serious side effects that can cause death. See "What is the most important information I should know about NULOJIX?"

Common side effects of NULOJIX include:

- low red blood count (anemia)
- diarrhea
- kidney or bladder infection
- swollen legs, feet, or ankles
- constipation
- high blood pressure
- fever
- new kidney not working well
- cough
- nausea or vomiting
- headache
- low potassium or high potassium in your blood
- low white blood cell count

Tell your doctor about any side effect that bothers you or that does not go away. These are not all the possible side effects of NULOJIX. For more information, ask your doctor or pharmacist.

Call your doctor for medical advice about side effects. You may report side effects to FDA at 1-800-FDA-1088.

You may also report side effects to BMS at 1-800-321-1335.

General information about NULOJIX

Medicines are sometimes prescribed for purposes other than those listed in a Medication Guide. This Medication Guide summarizes the most important information about NULOJIX. If you would like more information about NULOJIX, talk with your doctor. You can ask your pharmacist or doctor for information about NULOJIX that is written for healthcare professionals.

For more information, go to www.NULOJIX.com or call 1-800-321-1335.

What are the ingredients in NULOJIX?

Active ingredient: belatacept

Inactive ingredients: monobasic sodium phosphate, sodium chloride, and sucrose

This Medication Guide has been approved by the U.S. Food and Drug Administration.

Bristol-Myers Squibb Company
Princeton, New Jersey 08543
U.S. License No. 1713
Rev September 2014

NULOJIX 250 mg per vial Representative Packaging

See How Supplied section for a complete list of available packages of NULOJIX.

Contains 1 Vial and 1 Syringe
NDC 0003-0371-13
Nulojix®
(belatacept)
Rx only
For Injection
For Intravenous Infusion
250 mg per vial
ONLY USE THE SILICONE-FREE DISPOSABLE SYRINGE INCLUDED IN THIS PACKAGE FOR RECONSTITUTION
Provide enclosed Medication Guide to the patient.
1-888-NULOJIX
www.nulojix.com
Bristol Myers Squibb